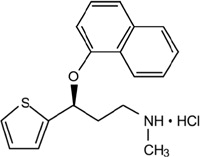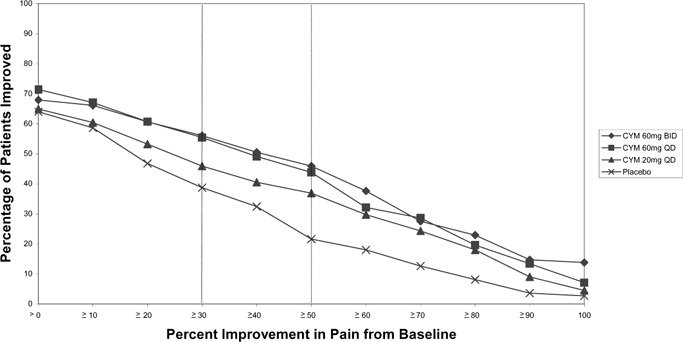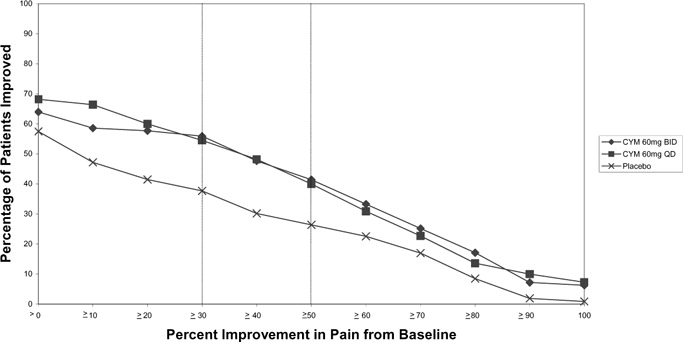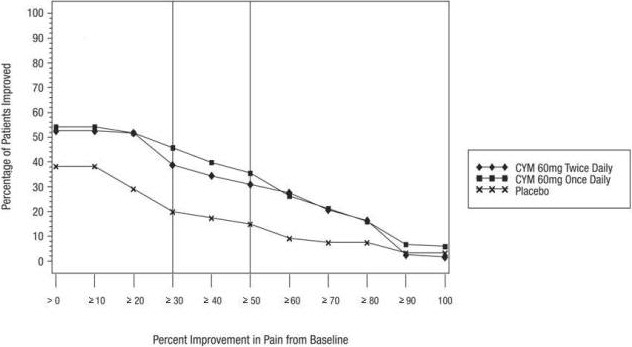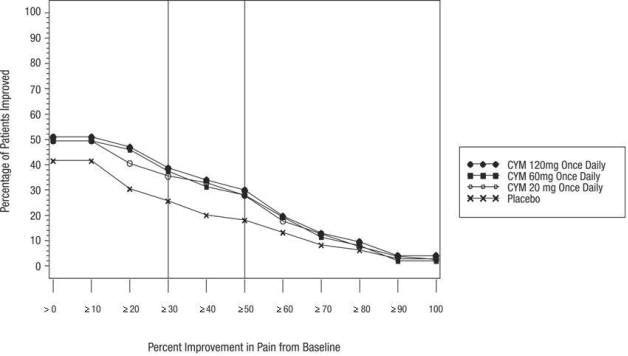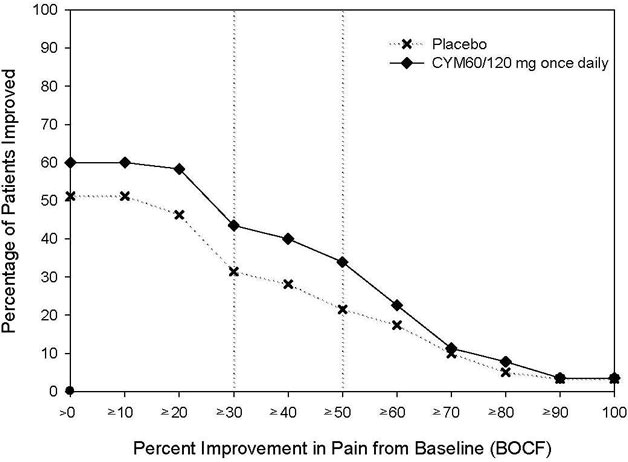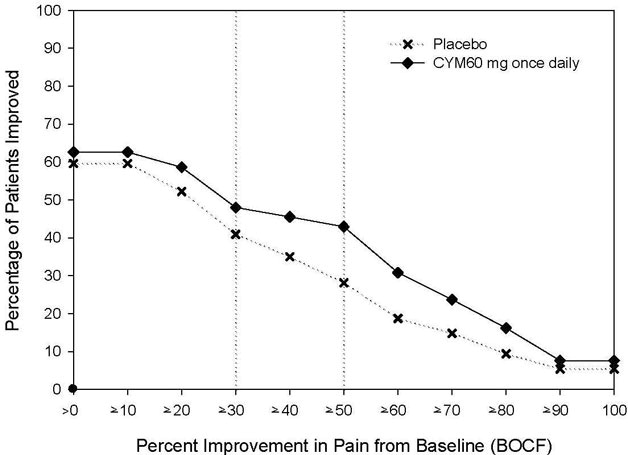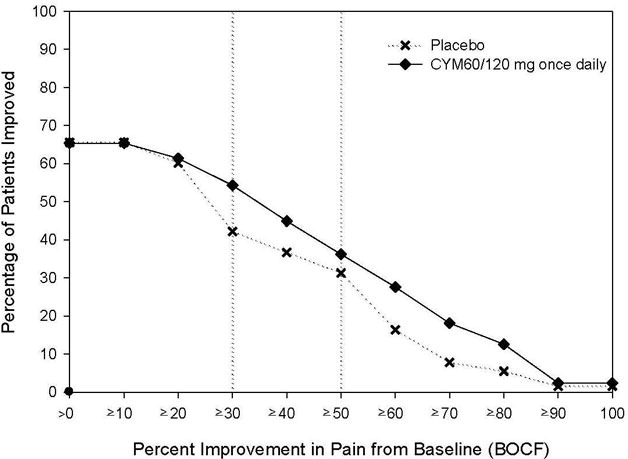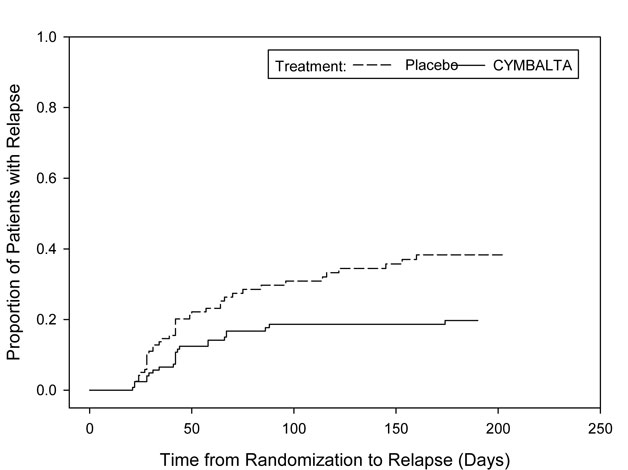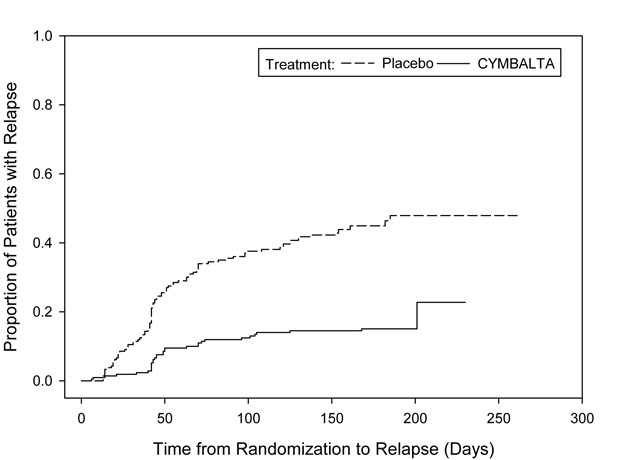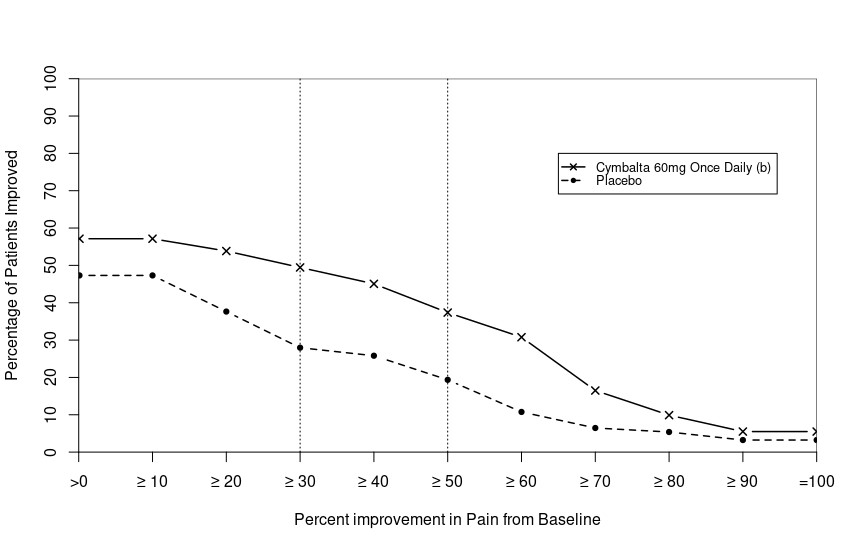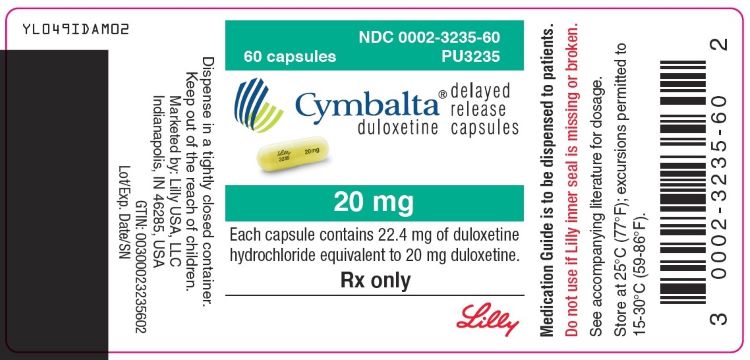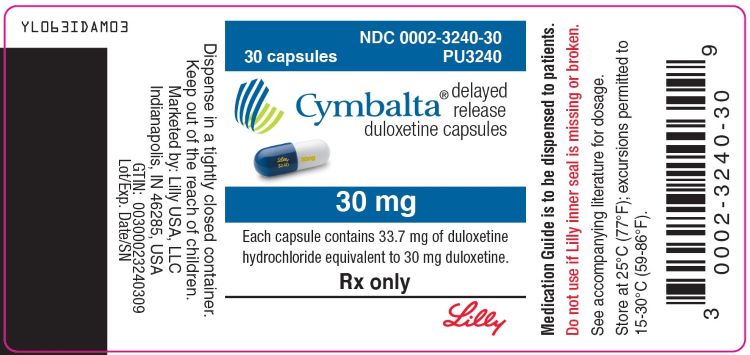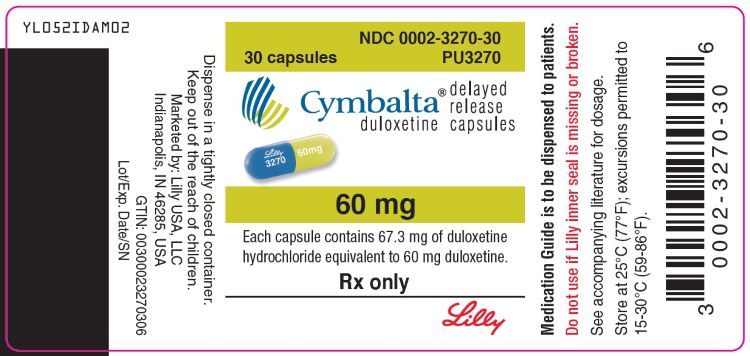 DRUG LABEL: Cymbalta
NDC: 0002-3235 | Form: CAPSULE, DELAYED RELEASE
Manufacturer: Eli Lilly and Company
Category: prescription | Type: HUMAN PRESCRIPTION DRUG LABEL
Date: 20250721

ACTIVE INGREDIENTS: Duloxetine hydrochloride 20 mg/1 1
INACTIVE INGREDIENTS: Gelatin, Unspecified; Hypromellose, Unspecified; Hypromellose Acetate Succinate 16070722 (3 MPA.S); Sodium lauryl sulfate; Sucrose; Talc; Titanium dioxide; Triethyl citrate; FD&C Blue No. 2; Ferric Oxide Yellow

HIGHLIGHTS OF PRESCRIBING INFORMATION

These highlights do not include all the information needed to use CYMBALTA safely and effectively. See full prescribing information for CYMBALTA.
CYMBALTA (duloxetine delayed-release capsules), for oral use
Initial U.S. Approval: 2004

RECENT MAJOR CHANGES

Warnings and Precautions (5.4, 5.5) | 08/2023

WARNING: SUICIDAL THOUGHTS AND BEHAVIORS

See full prescribing information for complete boxed warning.

- Increased risk of suicidal thinking and behavior in children, adolescents, and young adults taking antidepressants (5.1)
- Monitor for worsening and emergence of suicidal thoughts and behaviors (5.1)

1 INDICATIONS AND USAGE

CYMBALTA® is a serotonin and norepinephrine reuptake inhibitor (SNRI) indicated for the treatment of the following conditions:

- Major depressive disorder (MDD) in adults (1)
- Generalized anxiety disorder (GAD) in adults and pediatric patients 7 years of age and older (1)
- Diabetic peripheral neuropathic pain (DPNP) in adults (1)
- Fibromyalgia (FM) in adults and pediatric patients 13 years of age and older (1)
- Chronic musculoskeletal pain in adults (1)

2 DOSAGE AND ADMINISTRATION

- Take CYMBALTA once daily, with or without food. Swallow whole; do not crush, chew, or open capsule (2.1)

Indication | Starting Dose | Target Dose | Maximum Dose
MDD (2.2) | 40 mg/day to 60 mg/day | Acute Treatment: 40 mg/day (20 mg twice daily) to 60 mg/day (once daily or as 30 mg twice daily); Maintenance Treatment: 60 mg/day | 120 mg/day
GAD (2.3)
Adults | 60 mg/day | 60 mg/day (once daily) | 120 mg/day
Geriatric | 30 mg/day | 60 mg/day (once daily) | 120 mg/day
Pediatrics (7 to 17 years of age) | 30 mg/day | 30 to 60 mg/day (once daily) | 120 mg/day
DPNP (2.4) | 60 mg/day | 60 mg/day (once daily) | 60 mg/day
FM (2.5) | 30 mg/day | 60 mg/day (once daily) | 60 mg/day
Adults and Pediatrics (13 to 17 years of age)
Chronic Musculoskeletal Pain (2.6) | 30 mg/day | 60 mg/day (once daily) | 60 mg/day

- Discontinuing CYMBALTA: Gradually reduce dosage to avoid discontinuation symptoms (2.8, 5.7)

3 DOSAGE FORMS AND STRENGTHS

Delayed-release capsules: 20 mg, 30 mg, and 60 mg (3)

4 CONTRAINDICATIONS

- Concomitant use of an MAOI antidepressant with CYMBALTA is contraindicated
- Use of CYMBALTA within 14 days of stopping an MAOI antidepressant is contraindicated
- In linezolid- or intravenous methylene blue-treated patients, initiation of CYMBALTA is contraindicated (4)

5 WARNINGS AND PRECAUTIONS

- Hepatotoxicity: Hepatic failure, sometimes fatal, has been reported. Discontinue CYMBALTA in patients who develop jaundice or other evidence of clinically significant liver dysfunction and should not be resumed unless another cause can be established. Avoid use in patients with substantial alcohol use or evidence of chronic liver disease (5.2)
- Orthostatic Hypotension, Falls and Syncope: Consider dosage reduction or discontinuation if these events occur (5.3)
- Serotonin Syndrome: Increased risk when co-administered with other serotonergic agents, but also when taken alone. If it occurs, discontinue CYMBALTA and serotonergic agents (5.4)
- Increased Risk of Bleeding: May increase the risk of bleeding events. Concomitant use of antiplatelet drugs and anticoagulants may increase this risk (5.5, 7.4, 8.1)
- Severe Skin Reactions: Severe skin reactions, including erythema multiforme and Stevens-Johnson Syndrome (SJS), can occur; Discontinue at the first appearance of blisters, peeling rash, mucosal erosions, or any other sign of hypersensitivity if no other etiology can be identified (5.6)
- Activation of Mania or Hypomania: Prior to initiating, screen patients for personal or family history of bipolar disorder, mania, or hypomania (5.8)
- Angle-Closure Glaucoma: Has occurred in patients with untreated anatomically narrow angles treated with antidepressants (5.9)
- Seizures: Prescribe with care in patients with a history of seizure disorder (5.10)
- Blood Pressure Increases: Monitor blood pressure prior to initiating treatment and periodically throughout treatment (5.11)
- Inhibitors of CYP1A2 or Thioridazine: Avoid co-administration with CYMBALTA (5.12)
- Hyponatremia: Can occur in association with SIADH; consider discontinuation (5.13)
- Glucose Control in Diabetes: In DPNP patients, increases in fasting blood glucose, and HbA1c have been observed (5.14)
- Conditions that Slow Gastric Emptying: Use cautiously in these patients (5.14)
- Sexual Dysfunction: CYMBALTA may cause symptoms of sexual dysfunction (5.16)

6 ADVERSE REACTIONS

Most common adverse reactions (≥5% and at least twice the incidence of placebo-treated patients): (6.1)

Adults: nausea, dry mouth, somnolence, constipation, decreased appetite, and hyperhidrosis

Pediatric Patients: decreased weight, decreased appetite, nausea, vomiting, fatigue, and diarrhea

To report SUSPECTED ADVERSE REACTIONS, contact Eli Lilly and Company at 1-800-LillyRx (1-800-545-5979) or FDA at 1-800-FDA-1088 or www.fda.gov/medwatch.

7 DRUG INTERACTIONS

- Potent inhibitors of CYP1A2 should be avoided (7.1)
- Potent inhibitors of CYP2D6 may increase CYMBALTA concentrations (7.2)
- CYMBALTA is a moderate inhibitor of CYP2D6 (7.9)

8 USE IN SPECIFIC POPULATIONS

Pregnancy: Third trimester use may increase risk for symptoms of poor adaptation (respiratory distress, temperature instability, feeding difficulty, hypotonia, tremor, irritability) in the neonate (8.1)

Hepatic Impairment: Avoid use in patients with chronic liver disease or cirrhosis (5.14)

Renal Impairment: Avoid use in patients with severe renal impairment, GFR <30 mL/minute (5.14)

FULL PRESCRIBING INFORMATION

WARNING: SUICIDAL THOUGHTS AND BEHAVIORS

Antidepressants increased the risk of suicidal thoughts and behavior in children, adolescents, and young adults in short-term studies. These studies did not show an increase in the risk of suicidal thoughts and behavior with antidepressant use in patients over age 24; there was a reduction in risk with antidepressant use in patients aged 65 and older [see Warnings and Precautions (5.1)].

In patients of all ages who are started on antidepressant therapy, monitor closely for worsening, and for emergence of suicidal thoughts and behaviors. Advise families and caregivers of the need for close observation and communication with the prescriber [see Warnings and Precautions (5.1)].

1 INDICATIONS AND USAGE

CYMBALTA® is indicated for the treatment of:

- Major depressive disorder in adults
- Generalized anxiety disorder in adults and pediatric patients 7 years of age and older
- Diabetic peripheral neuropathic pain in adults
- Fibromyalgia in adults and pediatric patients 13 years of age and older
- Chronic musculoskeletal pain in adults

2 DOSAGE AND ADMINISTRATION

2.1 Important Administration Instructions

Administer CYMBALTA orally (with or without meals) and swallow whole. Do not chew or crush, and do not open the delayed-release capsule and sprinkle its contents on food or mix with liquids because these actions might affect the enteric coating. If a dose of CYMBALTA is missed, take the missed dose as soon as it is remembered. If it is almost time for the next dose, skip the missed dose and take the next dose at the regular time. Do not take two doses of CYMBALTA at the same time.

2.2 Dosage for Treatment of Major Depressive Disorder in Adults

The recommended starting dosage in adults with MDD is 40 mg/day (given as 20 mg twice daily) to 60 mg/day (given either once daily or as 30 mg twice daily). For some patients, it may be desirable to start at 30 mg once daily for 1 week, to allow patients to adjust to CYMBALTA before increasing to 60 mg once daily. While a 120 mg/day dose was shown to be effective, there is no evidence that doses greater than 60 mg/day confer any additional benefits. Periodically reassess to determine the need for maintenance treatment and the appropriate dosage for such treatment.

2.3 Dosage for Treatment of Generalized Anxiety Disorder

Recommended Dosage in Adults Less than 65 Years of Age

For most adults less than 65 years of age with GAD, initiate CYMBALTA 60 mg once daily. For some patients, it may be desirable to start at 30 mg once daily for 1 week, to allow patients to adjust to CYMBALTA before increasing to 60 mg once daily. While a 120 mg once daily dosage was shown to be effective, there is no evidence that doses greater than 60 mg/day confer additional benefit. Nevertheless, if a decision is made to increase the dosage beyond 60 mg once daily, increase dosage in increments of 30 mg once daily. Periodically reassess to determine the continued need for maintenance treatment and the appropriate dosage for such treatment.

Recommended Dosage in Geriatric Patients

In geriatric patients with GAD, initiate CYMBALTA at a dosage of 30 mg once daily for 2 weeks before considering an increase to the target dose of 60 mg/day. Thereafter, patients may benefit from doses above 60 mg once daily. If a decision is made to increase the dose beyond 60 mg once daily, increase dose in increments of 30 mg once daily. The maximum dose studied was 120 mg per day.

Recommended Dosage in Pediatric Patients 7 to 17 Years of Age

Initiate CYMBALTA in pediatric patients 7 to 17 years of age with GAD at a dosage of 30 mg once daily for 2 weeks before considering an increase to 60 mg once daily. The recommended dosage range is 30 to 60 mg once daily. Some patients may benefit from dosages above 60 mg once daily. If a decision is made to increase the dose beyond 60 mg once daily, increase dosage in increments of 30 mg once daily. The maximum dose studied was 120 mg per day.

2.4 Dosage for Treatment of Diabetic Peripheral Neuropathic Pain in Adults

Administer 60 mg once daily in adults with diabetic peripheral neuropathic pain. There is no evidence that doses higher than 60 mg once daily confer additional significant benefit and the higher dosage is clearly less well tolerated. For patients for whom tolerability is a concern, a lower starting dose may be considered.

Since diabetes is frequently complicated by renal disease, consider a lower starting dosage and gradual increase in dosage for patients with renal impairment [see Dosage and Administration (2.7) and Use in Specific Populations (8.10)].

2.5 Dosage for Treatment of Fibromyalgia

Recommended Dosage in Adults

The recommended CYMBALTA dosage is 60 mg once daily in adults with fibromyalgia. Begin treatment at 30 mg once daily for 1 week, to allow patients to adjust to CYMBALTA before increasing to 60 mg once daily. Some patients may respond to the starting dosage. There is no evidence that dosages greater than 60 mg/day confer additional benefit, even in patients who do not respond to a 60 mg/day dosage, and higher dosages were associated with a higher rate of adverse reactions.

Recommended Dosage in Pediatric Patients 13 to 17 Years of Age

The recommended starting CYMBALTA dosage in pediatric patients 13-17 years of age with fibromyalgia is 30 mg once daily. The dosage may be increased to 60 mg once daily based on response and tolerability.

2.6 Dosage for Treatment of Chronic Musculoskeletal Pain in Adults

The recommended CYMBALTA dosage is 60 mg once daily in adults with chronic musculoskeletal pain. Begin treatment at 30 mg once daily for one week, to allow patients to adjust to CYMBALTA before increasing to 60 mg once daily. There is no evidence that higher dosages confer additional benefit, even in patients who do not respond to a 60 mg once daily dosage, and higher dosages are associated with a higher rate of adverse reactions [see Clinical Studies (14.6)].

2.7 Dosage in Patients with Hepatic Impairment or Severe Renal Impairment

Avoid use in patients with chronic liver disease or cirrhosis [see Warnings and Precautions (5.14) and Use in Specific Populations (8.9)].

Avoid use in patients with severe renal impairment, GFR <30 mL/minute [see Warnings and Precautions (5.14) and Use in Specific Populations (8.10)].

2.8 Discontinuing CYMBALTA

Adverse reactions after discontinuation of CYMBALTA, after abrupt or tapered discontinuation, include: dizziness, headache, nausea, diarrhea, paresthesia, irritability, vomiting, insomnia, anxiety, hyperhidrosis, and fatigue. A gradual reduction in dosage rather than abrupt cessation is recommended whenever possible [see Warnings and Precautions (5.7)].

2.9 Switching a Patient to or from a Monoamine Oxidase Inhibitor (MAOI) Intended to Treat Psychiatric Disorders

At least 14 days should elapse between discontinuation of an MAOI intended to treat psychiatric disorders and initiation of therapy with CYMBALTA. Conversely, at least 5 days should be allowed after stopping CYMBALTA before starting an MAOI intended to treat psychiatric disorders [see Contraindications (4)].

2.10 Use of CYMBALTA with Other MAOIs such as Linezolid or Methylene Blue

Do not start CYMBALTA in a patient who is being treated with linezolid or intravenous methylene blue because there is an increased risk of serotonin syndrome. In a patient who requires more urgent treatment of a psychiatric condition, other interventions, including hospitalization, should be considered [see Contraindications (4)].

In some cases, a patient already receiving CYMBALTA therapy may require urgent treatment with linezolid or intravenous methylene blue. If acceptable alternatives to linezolid or intravenous methylene blue treatment are not available and the potential benefits of linezolid or intravenous methylene blue treatment are judged to outweigh the risks of serotonin syndrome in a particular patient, CYMBALTA should be stopped promptly, and linezolid or intravenous methylene blue can be administered. The patient should be monitored for symptoms of serotonin syndrome for 5 days or until 24 hours after the last dose of linezolid or intravenous methylene blue, whichever comes first. Therapy with CYMBALTA may be resumed 24 hours after the last dose of linezolid or intravenous methylene blue [see Warnings and Precautions (5.4)].

The risk of administering methylene blue by non-intravenous routes (such as oral tablets or by local injection) or in intravenous doses much lower than 1 mg/kg with CYMBALTA is unclear. The clinician should, nevertheless, be aware of the possibility of emergent symptoms of serotonin syndrome with such use [see Warnings and Precautions (5.4)].

3 DOSAGE FORMS AND STRENGTHS

CYMBALTA is available as delayed-release capsules:

- 20 mg opaque green capsules imprinted with “Lilly 3235 20mg”
- 30 mg opaque white and blue capsules imprinted with “Lilly 3240 30mg”
- 60 mg opaque green and blue capsules imprinted with “Lilly 3270 60mg”

4 CONTRAINDICATIONS

The use of MAOIs intended to treat psychiatric disorders with CYMBALTA or within 5 days of stopping treatment with CYMBALTA is contraindicated because of an increased risk of serotonin syndrome. The use of CYMBALTA within 14 days of stopping an MAOI intended to treat psychiatric disorders is contraindicated [see Dosage and Administration (2.8) and Warnings and Precautions (5.4)].

Starting CYMBALTA in a patient who is being treated with MAOIs such as linezolid or intravenous methylene blue is also contraindicated because of an increased risk of serotonin syndrome [see Dosage and Administration (2.9) and Warnings and Precautions (5.4)].

5 WARNINGS AND PRECAUTIONS

5.1 Suicidal Thoughts and Behaviors in Children, Adolescents, and Young Adults

Patients with major depressive disorder (MDD), both adult and pediatric, may experience worsening of their depression and/or the emergence of suicidal ideation and behavior (suicidality) or unusual changes in behavior, whether or not they are taking antidepressant medications, and this risk may persist until significant remission occurs. Suicide is a known risk of depression and certain other psychiatric disorders, and these disorders themselves are the strongest predictors of suicide. There has been a long-standing concern, however, that antidepressants may have a role in inducing worsening of depression and the emergence of suicidality in certain patients during the early phases of treatment.

Pooled analyses of short-term placebo-controlled trials of antidepressant drugs (SSRIs and others) showed that these drugs increase the risk of suicidal thinking and behavior (suicidality) in children, adolescents, and young adults (ages 18-24) with major depressive disorder (MDD) and other psychiatric disorders. Short-term studies did not show an increase in the risk of suicidality with antidepressants compared to placebo in adults beyond age 24; there was a reduction with antidepressants compared to placebo in adults aged 65 and older.

The pooled analyses of placebo-controlled trials in children and adolescents with MDD, obsessive compulsive disorder (OCD), or other psychiatric disorders included a total of 24 short-term trials of 9 antidepressant drugs in over 4400 patients. The pooled analyses of placebo-controlled trials in adults with MDD or other psychiatric disorders included a total of 295 short-term trials (median duration of 2 months) of 11 antidepressant drugs in over 77,000 patients. There was considerable variation in risk of suicidality among drugs, but a tendency toward an increase in the younger patients for almost all drugs studied. There were differences in absolute risk of suicidality across the different indications, with the highest incidence in MDD. The risk of differences (drug vs placebo), however, were relatively stable within age strata and across indications. These risk differences (drug-placebo difference in the number of cases of suicidality per 1000 patients treated) are provided in Table 1.

Table 1
Age Range | Drug-Placebo Difference in Number of Cases of Suicidality per 1000 Patients Treated
 | Increases Compared to Placebo
<18 | 14 additional cases
18-24 | 5 additional cases
 | Decreases Compared to Placebo
25-64 | 1 fewer case
≥65 | 6 fewer cases

No suicides occurred in any of the pediatric CYMBALTA trials. There were suicides in the adult CYMBALTA trials, but the number was not sufficient to reach any conclusion about CYMBALTA effect on suicide.

It is unknown whether the suicidality risk extends to longer-term use, i.e., beyond several months. However, there is substantial evidence from placebo-controlled maintenance trials in adults with depression that the use of antidepressants can delay the recurrence of depression.

All patients being treated with antidepressants for any indication should be monitored appropriately and observed closely for clinical worsening, suicidality, and unusual changes in behavior, especially during the initial few months of a course of drug therapy, or at times of dose changes, either increases or decreases.

The following symptoms, anxiety, agitation, panic attacks, insomnia, irritability, hostility, aggressiveness, impulsivity, akathisia (psychomotor restlessness), hypomania, and mania, have been reported in adult and pediatric patients being treated with antidepressants for major depressive disorder as well as for other indications, both psychiatric and nonpsychiatric. Although a causal link between the emergence of such symptoms and either the worsening of depression and/or the emergence of suicidal impulses has not been established, there is concern that such symptoms may represent precursors to emerging suicidality.

Consideration should be given to changing the therapeutic regimen, including possibly discontinuing the medication, in patients whose depression is persistently worse, or who are experiencing emergent suicidality or symptoms that might be precursors to worsening depression or suicidality, especially if these symptoms are severe, abrupt in onset, or were not part of the patient's presenting symptoms.

If the decision has been made to discontinue treatment, medication should be tapered, as rapidly as is feasible, but with recognition that discontinuation can be associated with certain symptoms [see Dosage and Administration (2.8) and Warnings and Precautions (5.7)] for descriptions of the risks of discontinuation of CYMBALTA.

Families and caregivers of patients being treated with antidepressants for major depressive disorder or other indications, both psychiatric and nonpsychiatric, should be alerted about the need to monitor patients for the emergence of agitation, irritability, unusual changes in behavior, and the other symptoms described above, as well as the emergence of suicidality, and to report such symptoms immediately to health care providers. Such monitoring should include daily observation by families and caregivers. Prescriptions for CYMBALTA should be written for the smallest quantity of capsules consistent with good patient management, in order to reduce the risk of overdose.

Screening Patients for Bipolar Disorder

A major depressive episode may be the initial presentation of bipolar disorder. It is generally believed (though not established in controlled trials) that treating such an episode with an antidepressant alone may increase the likelihood of precipitation of a mixed/manic episode in patients at risk for bipolar disorder. Whether any of the symptoms described above represent such a conversion is unknown. However, prior to initiating treatment with an antidepressant, patients with depressive symptoms should be adequately screened to determine if they are at risk for bipolar disorder; such screening should include a detailed psychiatric history, including a family history of suicide, bipolar disorder, and depression. It should be noted that CYMBALTA is not approved for use in treating bipolar depression.

5.2 Hepatotoxicity

There have been reports of hepatic failure, sometimes fatal, in patients treated with CYMBALTA. These cases have presented as hepatitis with abdominal pain, hepatomegaly, and elevation of transaminase levels to more than twenty times the upper limit of normal (ULN) with or without jaundice, reflecting a mixed or hepatocellular pattern of liver injury. CYMBALTA should be discontinued in patients who develop jaundice or other evidence of clinically significant liver dysfunction and should not be resumed unless another cause can be established.

Cases of cholestatic jaundice with minimal elevation of transaminase levels have also been reported. Other postmarketing reports indicate that elevated transaminases, bilirubin, and alkaline phosphatase have occurred in patients with chronic liver disease or cirrhosis.

CYMBALTA increased the risk of elevation of serum transaminase levels in development program clinical trials. Liver transaminase elevations resulted in the discontinuation of 0.3% (92/34,756) of CYMBALTA-treated patients. In most patients, the median time to detection of the transaminase elevation was about two months. In adult placebo-controlled trials, for patients with normal and abnormal baseline ALT values, elevation of ALT >3 times the ULN occurred in 1.25% (144/11,496) of CYMBALTA-treated patients compared to 0.45% (39/8716) of placebo-treated patients. In adult placebo-controlled studies using a fixed dose design, there was evidence of a CYMBALTA dose response relationship for ALT and AST elevation of >3 times the ULN and >5 times the ULN, respectively.

Because it is possible that CYMBALTA and alcohol may interact to cause liver injury or that CYMBALTA may aggravate pre-existing liver disease, CYMBALTA should not be prescribed to patients with substantial alcohol use or evidence of chronic liver disease.

5.3 Orthostatic Hypotension, Falls and Syncope

Orthostatic hypotension, falls, and syncope have been reported in patients treated with the recommended CYMBALTA dosages. Syncope and orthostatic hypotension tend to occur within the first week of therapy but can occur at any time during CYMBALTA treatment, particularly after dose increases. The risk of falling appears to be related to the degree of orthostatic decrease in blood pressure (BP) as well as other factors that may increase the underlying risk of falls.

In an analysis of patients from all placebo-controlled trials, patients treated with CYMBALTA reported a higher rate of falls compared to patients treated with placebo. Risk appears to be related to the presence of orthostatic decrease in BP. The risk of BP decreases may be greater in patients taking concomitant medications that induce orthostatic hypotension (such as antihypertensives) or are potent CYP1A2 inhibitors [see Warnings and Precautions (5.12) and Drug Interactions (7.1)] and in patients taking CYMBALTA at doses above 60 mg daily. Consideration should be given to dose reduction or discontinuation of CYMBALTA in patients who experience symptomatic orthostatic hypotension, falls and/or syncope during CYMBALTA therapy.

Risk of falling also appeared to be proportional to a patient's underlying risk for falls and appeared to increase steadily with age. As geriatric patients tend to have a higher underlying risk for falls due to a higher prevalence of risk factors such as use of multiple medications, medical comorbidities and gait disturbances, the impact of increasing age by itself is unclear. Falls with serious consequences including fractures and hospitalizations have been reported with CYMBALTA use [see Adverse Reactions (6.1)].

5.4 Serotonin Syndrome

Serotonin-norepinephrine reuptake inhibitors (SNRIs), including CYMBALTA, can precipitate serotonin syndrome, a potentially life-threatening condition. The risk is increased with concomitant use of other serotonergic drugs (including triptans, tricyclic antidepressants, fentanyl, lithium, tramadol, meperidine, methadone, tryptophan, buspirone, amphetamines, and St. John's Wort) and with drugs that impair metabolism of serotonin, i.e., MAOIs, [see Contraindications (4), Drug Interactions (7.13)]. Serotonin syndrome can also occur when these drugs are used alone.

Serotonin syndrome signs and symptoms may include mental status changes (e.g., agitation, hallucinations, delirium, and coma), autonomic instability (e.g., tachycardia, labile blood pressure, dizziness, diaphoresis, flushing, hyperthermia), neuromuscular symptoms (e.g., tremor, rigidity, myoclonus, hyperreflexia, incoordination), seizures, and gastrointestinal symptoms (e.g., nausea, vomiting, diarrhea).

The concomitant use of CYMBALTA with MAOIs is contraindicated. In addition, do not initiate CYMBALTA in a patient being treated with MAOIs such as linezolid or intravenous methylene blue. No reports involved the administration of methylene blue by other routes (such as oral tablets or local tissue injection). If it is necessary to initiate treatment with an MAOI such as linezolid or intravenous methylene blue in a patient taking CYMBALTA, discontinue CYMBALTA before initiating treatment with the MAOI [see Contraindications (4) and Drug Interactions (7.13)].

Monitor all patients taking CYMBALTA for the emergence of serotonin syndrome. Discontinue treatment with CYMBALTA and any concomitant serotonergic agents immediately if the above symptoms occur, and initiate supportive symptomatic treatment. If concomitant use of CYMBALTA with other serotonergic drugs is clinically warranted, inform patients of the increased risk for serotonin syndrome and monitor for symptoms.

5.5 Increased Risk of Bleeding

Drugs that interfere with serotonin reuptake inhibition, including CYMBALTA, may increase the risk of bleeding events. Case reports and epidemiological studies (case-control and cohort design) have demonstrated an association between use of drugs that interfere with serotonin reuptake and the occurrence of gastrointestinal bleeding. A post-marketing study showed a higher incidence of postpartum hemorrhage in mothers taking CYMBALTA. Other bleeding events related to SSRI and SNRI use have ranged from ecchymoses, hematomas, epistaxis, and petechiae to life-threatening hemorrhages. Concomitant use of aspirin, nonsteroidal anti-inflammatory drugs (NSAIDs), warfarin, and other anti-coagulants may add to this risk.

Inform patients about the risk of increased bleeding associated with the concomitant use of CYMBALTA and NSAIDs, aspirin, or other drugs that affect coagulation [see Drug Interactions (7.4)].

5.6 Severe Skin Reactions

Severe skin reactions, including erythema multiforme and Stevens-Johnson Syndrome (SJS), can occur with CYMBALTA. The reporting rate of SJS associated with CYMBALTA use exceeds the general population background incidence rate for this serious skin reaction (1 to 2 cases per million person years). The reporting rate is generally accepted to be an underestimate due to underreporting.

CYMBALTA should be discontinued at the first appearance of blisters, peeling rash, mucosal erosions, or any other sign of hypersensitivity if no other etiology can be identified.

5.7 Discontinuation Syndrome

Discontinuation symptoms have been systematically evaluated in patients taking CYMBALTA. Following abrupt or tapered discontinuation in adult placebo-controlled clinical trials, the following symptoms occurred at 1% or greater and at a significantly higher rate in CYMBALTA-treated patients compared to those discontinuing from placebo: dizziness, headache, nausea, diarrhea, paresthesia, irritability, vomiting, insomnia, anxiety, hyperhidrosis, and fatigue.

During marketing of other SSRIs and SNRIs (serotonin and norepinephrine reuptake inhibitors), there have been spontaneous reports of adverse events occurring upon discontinuation of these drugs, particularly when abrupt, including the following: dysphoric mood, irritability, agitation, dizziness, sensory disturbances (e.g., paresthesias such as electric shock sensations), anxiety, confusion, headache, lethargy, emotional lability, insomnia, hypomania, tinnitus, and seizures. Although these events are generally self-limiting, some have been reported to be severe.

Patients should be monitored for these symptoms when discontinuing treatment with CYMBALTA. A gradual reduction in the dose rather than abrupt cessation is recommended whenever possible. If intolerable symptoms occur following a decrease in the dose or upon discontinuation of treatment, then resuming the previously prescribed dose may be considered. Subsequently, the healthcare provider may continue decreasing the dose but at a more gradual rate [see Dosage and Administration (2.8)].

5.8 Activation of Mania/Hypomania

In adult placebo-controlled trials in patients with MDD, activation of mania or hypomania was reported in 0.1% (4/3779) of CYMBALTA-treated patients and 0.04% (1/2536) of placebo-treated patients. No activation of mania or hypomania was reported in DPNP, GAD, fibromyalgia, or chronic musculoskeletal pain placebo-controlled trials. Activation of mania or hypomania has been reported in a small proportion of patients with mood disorders who were treated with other marketed drugs effective in the treatment of major depressive disorder. As with these other agents, CYMBALTA should be used cautiously in patients with a history of mania.

5.9 Angle-Closure Glaucoma

The pupillary dilation that occurs following use of many antidepressant drugs including CYMBALTA may trigger an angle closure attack in a patient with anatomically narrow angles who does not have a patent iridectomy.

5.10 Seizures

CYMBALTA has not been systematically evaluated in patients with a seizure disorder, and such patients were excluded from clinical studies. In adult placebo-controlled clinical trials, seizures/convulsions occurred in 0.02% (3/12,722) of patients treated with CYMBALTA and 0.01% (1/9513) of patients treated with placebo. CYMBALTA should be prescribed with care in patients with a history of a seizure disorder.

5.11 Increases in Blood Pressure

In adult placebo-controlled clinical trials across the approved adult populations from baseline to endpoint, CYMBALTA treatment was associated with mean increases of 0.5 mm Hg in systolic blood pressure and 0.8 mm Hg in diastolic blood pressure compared to mean decreases of 0.6 mm Hg systolic and 0.3 mm Hg diastolic in placebo-treated patients. There was no significant difference in the frequency of sustained (3 consecutive visits) elevated blood pressure. In a clinical pharmacology study designed to evaluate the effects of CYMBALTA on various parameters, including blood pressure at supratherapeutic doses with an accelerated dose titration, there was evidence of increases in supine blood pressure at doses up to 200 mg twice daily (approximately 3.3 times the maximum recommended dosage). At the highest 200 mg twice daily dose, the increase in mean pulse rate was 5.0 to 6.8 beats and increases in mean blood pressure were 4.7 to 6.8 mm Hg (systolic) and 4.5 to 7 mm Hg (diastolic) up to 12 hours after dosing.

Blood pressure should be measured prior to initiating treatment and periodically measured throughout treatment [see Adverse Reactions (6.1)].

5.12 Clinically Important Drug Interactions

Both CYP1A2 and CYP2D6 are responsible for CYMBALTA metabolism.

Potential for Other Drugs to Affect CYMBALTA

CYP1A2 Inhibitors — Co-administration of CYMBALTA with potent CYP1A2 inhibitors should be avoided [see Drug Interactions (7.1)].

CYP2D6 Inhibitors — Because CYP2D6 is involved in CYMBALTA metabolism, concomitant use of CYMBALTA with potent inhibitors of CYP2D6 would be expected to, and does, result in higher concentrations (on average of 60%) of CYMBALTA [see Drug Interactions (7.2)].

Potential for CYMBALTA to Affect Other Drugs

Drugs Metabolized by CYP2D6 — Co-administration of CYMBALTA with drugs that are extensively metabolized by CYP2D6 and that have a narrow therapeutic index, including certain antidepressants (tricyclic antidepressants [TCAs], such as nortriptyline, amitriptyline, and imipramine), phenothiazines and Type 1C antiarrhythmics (e.g., propafenone, flecainide), should be approached with caution. Plasma TCA concentrations may need to be monitored and the dose of the TCA may need to be reduced if a TCA is co-administered with CYMBALTA. Because of the risk of serious ventricular arrhythmias and sudden death potentially associated with elevated plasma levels of thioridazine, CYMBALTA and thioridazine should not be co-administered [see Drug Interactions (7.9)].

Other Clinically Important Drug Interactions

Alcohol — Use of CYMBALTA concomitantly with heavy alcohol intake may be associated with severe liver injury. For this reason, CYMBALTA should not be prescribed for patients with substantial alcohol use [see Warnings and Precautions (5.2) and Drug Interactions (7.15)].

CNS Acting Drugs — Given the primary CNS effects of CYMBALTA, it should be used with caution when it is taken in combination with or substituted for other centrally acting drugs, including those with a similar mechanism of action [see Warnings and Precautions (5.12) and Drug Interactions (7.16)].

5.13 Hyponatremia

Hyponatremia may occur as a result of treatment with SSRIs and SNRIs, including CYMBALTA. In many cases, this hyponatremia appears to be the result of the syndrome of inappropriate antidiuretic hormone secretion (SIADH). Cases with serum sodium lower than 110 mmol/L have been reported with CYMBALTA use and appeared to be reversible when CYMBALTA was discontinued. Geriatric patients may be at greater risk of developing hyponatremia with SSRIs and SNRIs. Also, patients taking diuretics or who are otherwise volume depleted may be at greater risk [see Use in Specific Populations (8.5)]. Discontinuation of CYMBALTA should be considered in patients with symptomatic hyponatremia and appropriate medical intervention should be instituted.

Signs and symptoms of hyponatremia include headache, difficulty concentrating, memory impairment, confusion, weakness, and unsteadiness, which may lead to falls. More severe and/or acute cases have been associated with hallucination, syncope, seizure, coma, respiratory arrest, and death.

5.14 Use in Patients with Concomitant Illness

Clinical experience with CYMBALTA in patients with concomitant systemic illnesses is limited. There is no information on the effect that alterations in gastric motility may have on the stability of CYMBALTA's enteric coating. In extremely acidic conditions, CYMBALTA, unprotected by the enteric coating, may undergo hydrolysis to form naphthol. Caution is advised in using CYMBALTA in patients with conditions that may slow gastric emptying (e.g., some diabetics).

CYMBALTA has not been systematically evaluated in patients with a recent history of myocardial infarction or unstable coronary artery disease. Patients with these diagnoses were generally excluded from clinical studies during the product's premarketing testing.

Hepatic Impairment

Avoid use in patients with chronic liver disease or cirrhosis [see Dosage and Administration (2.7), Warnings and Precautions (5.2), and Use in Specific Populations (8.9)].

Severe Renal Impairment

Avoid use in patients with severe renal impairment, GFR <30 mL/minute. Increased plasma concentration of CYMBALTA, and especially of its metabolites, occurred in patients with end-stage renal disease (requiring dialysis) [see Dosage and Administration (2.7) and Use in Specific Populations (8.10)].

Glycemic Control in Patients with Diabetes

As observed in DPNP trials, CYMBALTA treatment worsened glycemic control in some patients with diabetes. In three clinical trials of CYMBALTA for the management of neuropathic pain associated with diabetic peripheral neuropathy [see Clinical Studies (14.4)], the mean duration of diabetes was approximately 12 years, the mean baseline fasting blood glucose was 176 mg/dL, and the mean baseline hemoglobin A1c (HbA1c) was 7.8%. In the 12-week acute treatment phase of these studies, CYMBALTA was associated with a small increase in mean fasting blood glucose as compared to placebo. In the extension phase of these studies, which lasted up to 52 weeks, mean fasting blood glucose increased by 12 mg/dL in the CYMBALTA group and decreased by 11.5 mg/dL in the routine care group. HbA1c increased by 0.5% in the CYMBALTA group and by 0.2% in the routine care group.

5.15 Urinary Hesitation and Retention

CYMBALTA is in a class of drugs known to affect urethral resistance. If symptoms of urinary hesitation develop during treatment with CYMBALTA, consideration should be given to the possibility that they might be drug-related.

In post marketing experience, cases of urinary retention have been observed. In some instances of urinary retention associated with CYMBALTA use, hospitalization and/or catheterization has been needed.

5.16 Sexual Dysfunction

Use of SNRIs, including CYMBALTA, may cause symptoms of sexual dysfunction [see Adverse Reactions (6.1)]. In male patients, SNRI use may result in ejaculatory delay or failure, decreased libido, and erectile dysfunction. In female patients, SNRI use may result in decreased libido and delayed or absent orgasm.

It is important for prescribers to inquire about sexual function prior to initiation of CYMBALTA and to inquire specifically about changes in sexual function during treatment, because sexual function may not be spontaneously reported. When evaluating changes in sexual function, obtaining a detailed history (including timing of symptom onset) is important because sexual symptoms may have other causes, including the underlying psychiatric disorder. Discuss potential management strategies to support patients in making informed decisions about treatment.

6 ADVERSE REACTIONS

The following serious adverse reactions are described below and elsewhere in the labeling:

- Suicidal Thoughts and Behaviors in Children, Adolescents, and Young Adults [see Boxed Warning and Warnings and Precautions (5.1)]
- Hepatotoxicity [see Warnings and Precautions (5.2)]
- Orthostatic Hypotension, Falls and Syncope [see Warnings and Precautions (5.3)]
- Serotonin Syndrome [see Warnings and Precautions (5.4)]
- Increased Risk of Bleeding [see Warnings and Precautions (5.5)]
- Severe Skin Reactions [see Warnings and Precautions (5.6)]
- Discontinuation Syndrome [see Warnings and Precautions (5.7)]
- Activation of Mania/Hypomania [see Warnings and Precautions (5.8)]
- Angle-Closure Glaucoma [see Warnings and Precautions (5.9)]
- Seizures [see Warnings and Precautions (5.10)]
- Increases in Blood Pressure [see Warnings and Precautions (5.11)]
- Clinically Important Drug Interactions [see Warnings and Precautions (5.12)]
- Hyponatremia [see Warnings and Precautions (5.13)]
- Urinary Hesitation and Retention [see Warnings and Precautions (5.15)]
- Sexual Dysfunction [see Warnings and Precautions (5.16)]

6.1 Clinical Trials Experience

Because clinical trials are conducted under widely varying conditions, adverse reaction rates observed in the clinical trials of a drug cannot be directly compared to rates in the clinical trials of another drug and may not reflect the rates observed in practice.

The stated frequencies of adverse reactions represent the proportion of patients who experienced, at least once, one treatment-emergent adverse reaction of the type listed. A reaction was considered treatment-emergent if it occurred for the first time or worsened while receiving therapy following baseline evaluation.

Adverse Reactions in Adults

Adult Clinical Trial Database

The data described below reflect exposure to CYMBALTA in placebo-controlled adult trials for MDD (N=3779), GAD (N=1018), OA (N=503), CLBP (N=600), DPNP (N=906), and FM (N=1294). The age range in this pooled population was 17 to 89 years of age. In this pooled population, 66%, 61%, 61%, 43%, and 94% of adult patients were female; and 82%, 73%, 85%, 74%, and 86% of adult patients were Caucasian in the MDD, GAD, OA and CLBP, DPNP, and FM populations, respectively. Most patients received CYMBALTA dosages of a total of 60 to 120 mg per day [see Clinical Studies (14)]. The data below do not include results of the trial that evaluated the efficacy of CYMBALTA for the treatment of GAD in patients ≥65 years old (Study GAD-5) [see Clinical Studies (14.3)]; however, the adverse reactions observed in this geriatric population were generally similar to adverse reactions in the overall adult population.

Adverse Reactions Leading to Treatment Discontinuation in Adult Placebo-Controlled Trials

Major Depressive Disorder

Approximately 8.4% (319/3779) of CYMBALTA-treated patients in placebo-controlled adult trials for MDD discontinued treatment due to an adverse reaction, compared with 4.6% (117/2536) of placebo-treated patients. Nausea (CYMBALTA 1.1%, placebo 0.4%) was the only adverse reaction reported as a reason for discontinuation and considered to be drug-related (i.e., discontinuation occurring in at least 1% of the CYMBALTA-treated patients and at a rate of at least twice that of placebo-treated patients).

Generalized Anxiety Disorder

Approximately 13.7% (139/1018) of the CYMBALTA-treated patients in placebo-controlled adult trials for GAD discontinued treatment due to an adverse reaction, compared with 5% (38/767) for placebo-treated patients. Common adverse reactions reported as a reason for discontinuation and considered to be drug-related (as defined above) included nausea (CYMBALTA 3.3%, placebo 0.4%), and dizziness (CYMBALTA 1.3%, placebo 0.4%).

Diabetic Peripheral Neuropathic Pain

Approximately 12.9% (117/906) of the CYMBALTA-treated patients in placebo-controlled adult trials for DPNP discontinued treatment due to an adverse reaction, compared with 5.1% (23/448) for placebo-treated patients. Common adverse reactions reported as a reason for discontinuation and considered to be drug-related (as defined above) included nausea (CYMBALTA 3.5%, placebo 0.7%), dizziness (CYMBALTA 1.2%, placebo 0.4%), and somnolence (CYMBALTA 1.1%, placebo 0%).

Fibromyalgia

Approximately 17.5% (227/1294) of the CYMBALTA-treated patients in 3- to 6-month placebo-controlled adult trials for FM discontinued treatment due to an adverse reaction, compared with 10.1% (96/955) for placebo-treated patients. Adverse reactions reported as a reason for discontinuation and considered to be drug-related (as defined above) included nausea (CYMBALTA 2.0%, placebo 0.5%), headache (CYMBALTA 1.2%, placebo 0.3%), somnolence (CYMBALTA 1.1%, placebo 0%), and fatigue (CYMBALTA 1.1%, placebo 0.1%).

Chronic Pain due to Osteoarthritis

Approximately 15.7% (79/503) of the CYMBALTA-treated patients in 13-week, placebo-controlled adult trials for chronic pain due to OA discontinued treatment due to an adverse reaction, compared with 7.3% (37/508) for placebo-treated patients. Adverse reactions reported as a reason for discontinuation and considered to be drug-related (as defined above) included nausea (CYMBALTA 2.2%, placebo 1%).

Chronic Low Back Pain

Approximately 16.5% (99/600) of the CYMBALTA-treated patients in 13-week, placebo-controlled adult trials for CLBP discontinued treatment due to an adverse reaction, compared with 6.3% (28/441) for placebo-treated patients. Adverse reactions reported as a reason for discontinuation and considered to be drug-related (as defined above) included nausea (CYMBALTA 3%, placebo 0.7%), and somnolence (CYMBALTA 1%, placebo 0%).

Most Common Adverse Reactions in Adult Trials

The most commonly observed adverse reactions in CYMBALTA-treated patients (as defined above) were:

- Diabetic Peripheral Neuropathic Pain: nausea, somnolence, decreased appetite, constipation, hyperhidrosis, and dry mouth.
- Fibromyalgia: nausea, dry mouth, constipation, somnolence, decreased appetite, hyperhidrosis, and agitation.
- Chronic Pain due to Osteoarthritis: nausea, fatigue, constipation, dry mouth, insomnia, somnolence, and dizziness.
- Chronic Low Back Pain: nausea, dry mouth, insomnia, somnolence, constipation, dizziness, and fatigue.

The most commonly observed adverse reactions in CYMBALTA-treated patients in all the pooled adult populations (i.e., MDD, GAD, DPNP, FM, OA, and CLBP) (incidence of at least 5% and at least twice the incidence in placebo-treated patients) were nausea, dry mouth, somnolence, constipation, decreased appetite, and hyperhidrosis.

Table 2 displays the incidence of adverse reactions in placebo-controlled trials for approved adult populations (i.e., MDD, GAD, DPNP, FM, OA, and CLBP) that occurred in 5% or more of CYMBALTA-treated patients and with an incidence greater than placebo-treated patients.

Table 2: Adverse Reactions: Incidence of 5% or More and Greater than Placebo in Placebo-Controlled Trials of Approved Adult Populationsa
Adverse Reaction | Percentage of Patients Reporting Reaction
Adverse Reaction | CYMBALTA (N=8100) | Placebo (N=5655)
Nauseac | 23 | 8
Headache | 14 | 12
Dry mouth | 13 | 5
Somnolencee | 10 | 3
Fatigueb,c | 9 | 5
Insomniad | 9 | 5
Constipationc | 9 | 4
Dizzinessc | 9 | 5
Diarrhea | 9 | 6
Decreased appetitec | 7 | 2
Hyperhidrosisc | 6 | 1
Abdominal painf | 5 | 4
a Includes adults with MDD, GAD, DPNP, FM, and chronic musculoskeletal pain. The inclusion of an event in the table is determined based on the percentages before rounding; however, the percentages displayed in the table are rounded to the nearest integer.
b Also includes asthenia.
c Events for which there was a significant dose-dependent relationship in fixed-dose studies, excluding three MDD studies which did not have a placebo lead-in period or dose titration.
d Also includes initial insomnia, middle insomnia, and early morning awakening.
e Also includes hypersomnia and sedation.
f Also includes abdominal discomfort, abdominal pain lower, abdominal pain upper, abdominal tenderness, and gastrointestinal pain.

Adverse Reactions in Pooled MDD and GAD Trials in Adults

Table 3 displays the incidence of adverse reactions in MDD and GAD placebo-controlled adult trials that occurred in 2% or more of CYMBALTA-treated patients and with an incidence greater than placebo-treated patients.

Table 3: Adverse Reactions: Incidence of 2% or More and Greater than Placebo in MDD and GAD Placebo-Controlled Trials in Adultsa,b
System Organ Class / Adverse Reaction | Percentage of Patients Reporting Reaction
System Organ Class / Adverse Reaction | CYMBALTA (N=4797) | Placebo (N=3303)
Cardiac Disorders
Palpitations | 2 | 1
Eye Disorders
Vision blurred | 3 | 1
Gastrointestinal Disorders
Nauseac | 23 | 8
Dry mouth | 14 | 6
Constipationc | 9 | 4
Diarrhea | 9 | 6
Abdominal paind | 5 | 4
Vomiting | 4 | 2
General Disorders and Administration Site Conditions
Fatiguee | 9 | 5
Metabolism and Nutrition Disorders
Decreased appetitec | 6 | 2
Nervous System Disorders
Headache | 14 | 14
Dizzinessc | 9 | 5
Somnolencef | 9 | 3
Tremor | 3 | 1
Psychiatric Disorders
Insomniag | 9 | 5
Agitationh | 4 | 2
Anxiety | 3 | 2
Reproductive System and Breast Disorders
Erectile dysfunction | 4 | 1
Ejaculation delayedc | 2 | 1
Libido decreasedi | 3 | 1
Orgasm abnormalj | 2 | <1
Respiratory, Thoracic, and Mediastinal Disorders
Yawning | 2 | <1
Skin and Subcutaneous Tissue Disorders
Hyperhidrosis | 6 | 2
a The inclusion of an event in the table is determined based on the percentages before rounding; however, the percentages displayed in the table are rounded to the nearest integer.
b For GAD, there were no adverse reactions that were significantly different between treatments in adults ≥65 years that were also not significant in the adults <65 years.
c Events for which there was a significant dose-dependent relationship in fixed-dose studies, excluding three MDD studies which did not have a placebo lead-in period or dose titration.
d Includes abdominal pain upper, abdominal pain lower, abdominal tenderness, abdominal discomfort, and gastrointestinal pain.
e Includes asthenia.
f Includes hypersomnia and sedation.
g Includes initial insomnia, middle insomnia, and early morning awakening.
h Includes feeling jittery, nervousness, restlessness, tension and psychomotor hyperactivity.
i Includes loss of libido.
j Includes anorgasmia.

Adverse Reactions in the DPNP, FM, OA, and CLBP Adult Trials

Table 4 displays the incidence of adverse reactions that occurred in 2% or more of CYMBALTA-treated patients (determined prior to rounding) in the premarketing acute phase of DPNP, FM, OA, and CLBP placebo-controlled adult trials and with an incidence greater than placebo-treated patients.

Table 4: Adverse Reactions: Incidence of 2% or More and Greater than Placebo in DPNP, FM, OA, and CLBP Placebo-Controlled Trialsa
System Organ Class / Adverse Reaction | Percentage of Patients Reporting Reaction
System Organ Class / Adverse Reaction | CYMBALTA (N=3303) | Placebo (N=2352)
Gastrointestinal Disorders
Nausea | 23 | 7
Dry Mouthb | 11 | 3
Constipationb | 10 | 3
Diarrhea | 9 | 5
Abdominal Painc | 5 | 4
Vomiting | 3 | 2
Dyspepsia | 2 | 1
General Disorders and Administration Site Conditions
Fatigued | 11 | 5
Infections and Infestations
Nasopharyngitis | 4 | 4
Upper Respiratory Tract Infection | 3 | 3
Influenza | 2 | 2
Metabolism and Nutrition Disorders
Decreased Appetiteb | 8 | 1
Musculoskeletal and Connective Tissue
Musculoskeletal Paine | 3 | 3
Muscle Spasms | 2 | 2
Nervous System Disorders
Headache | 13 | 8
Somnolenceb,f | 11 | 3
Dizziness | 9 | 5
Paraesthesiag | 2 | 2
Tremorb | 2 | <1
Psychiatric Disorders
Insomniab,h | 10 | 5
Agitationi | 3 | 1
Reproductive System and Breast Disorders
Erectile Dysfunctionb | 4 | <1
Ejaculation Disorderj | 2 | <1
Respiratory, Thoracic, and Mediastinal Disorders
Cough | 2 | 2
Skin and Subcutaneous Tissue Disorders
Hyperhidrosis | 6 | 1
Vascular Disorders
Flushingk | 3 | 1
Blood pressure increasedl | 2 | 1
a The inclusion of an event in the table is determined based on the percentages before rounding; however, the percentages displayed in the table are rounded to the nearest integer.
b Incidence of 120 mg/day is significantly greater than the incidence for 60 mg/day.
c Includes abdominal discomfort, lower abdominal pain, upper abdominal pain, abdominal tenderness and gastrointestinal pain.
d Includes asthenia.
e Includes myalgia and neck pain.
f Includes hypersomnia and sedation.
g Includes hypoaesthesia, facial hypoaesthesia, genital hypoaesthesia and oral paraesthesia.
h Includes initial insomnia, middle insomnia, and early morning awakening.
i Includes feeling jittery, nervousness, restlessness, tension and psychomotor hyperactivity.
j Includes ejaculation failure.
k Includes hot flush.
l Includes increased diastolic blood pressure, increased systolic blood pressure, diastolic hypertension, essential hypertension, hypertension, hypertensive crisis, labile hypertension, orthostatic hypertension, secondary hypertension, and systolic hypertension.

Effects on Male and Female Sexual Function in Adults with MDD

Changes in sexual desire, sexual performance and sexual satisfaction often occur as manifestations of psychiatric disorders or diabetes, but they may also be a consequence of pharmacologic treatment. Because adverse sexual reactions are presumed to be voluntarily underreported, the Arizona Sexual Experience Scale (ASEX), a validated measure designed to identify sexual adverse reactions, was used prospectively in 4 MDD placebo-controlled adult trials (Studies MDD-1, MDD-2, MDD-3, and MDD-4) [see Clinical Studies (14.2)]. The ASEX scale includes five questions that pertain to the following aspects of sexual function: 1) sex drive, 2) ease of arousal, 3) ability to achieve erection (men) or lubrication (women), 4) ease of reaching orgasm, and 5) orgasm satisfaction. Positive numbers signify a worsening of sexual function from baseline. Negative numbers signify an improvement from a baseline level of dysfunction, which is commonly seen in depressed patients.

In these trials, CYMBALTA-treated male patients experienced significantly more sexual dysfunction, as measured by the total score on the ASEX and the ability to reach orgasm, than placebo-treated male patients (see Table 5). CYMBALTA-treated female patients did not experience more sexual dysfunction than placebo-treated female patients as measured by ASEX total score. Healthcare providers should routinely inquire about possible sexual adverse reactions in CYMBALTA-treated patients.

Table 5: Mean Change in ASEX Scores by Gender in MDD Placebo-Controlled Adult Trials
 | Male Patientsa |  | Female Patientsa
 | CYMBALTA (n=175) | Placebo (n=83) | CYMBALTA (n=241) | Placebo (n=126)
ASEX Total (Items 1-5) | 0.56b | -1.07 | -1.15 | -1.07
Item 1 — Sex drive | -0.07 | -0.12 | -0.32 | -0.24
Item 2 — Arousal | 0.01 | -0.26 | -0.21 | -0.18
Item 3 — Ability to achieve erection (men); Lubrication (women) | 0.03 | -0.25 | -0.17 | -0.18
Item 4 — Ease of reaching orgasm | 0.40c | -0.24 | -0.09 | -0.13
Item 5 — Orgasm satisfaction | 0.09 | -0.13 | -0.11 | -0.17
a n=Number of patients with non-missing change score for ASEX total.
b p=0.013 versus placebo.
c p<0.001 versus placebo.

Vital Sign Changes in Adults

In placebo-controlled clinical trials across approved adult populations for change from baseline to endpoint, CYMBALTA-treated patients had mean increases of 0.23 mm Hg in systolic blood pressure (SBP) and 0.73 mm Hg in diastolic blood pressure (DBP) compared to mean decreases of 1.09 mm Hg in SBP and 0.55 mm Hg in DBP in placebo-treated patients. There was no significant difference in the frequency of sustained (3 consecutive visits) elevated blood pressure [see Warnings and Precautions (5.3, 5.11)].

CYMBALTA treatment, for up to 26 weeks in placebo-controlled trials across approved adult populations, typically caused a small increase in heart rate for change from baseline to endpoint compared to placebo of up to 1.37 beats per minute (increase of 1.20 beats per minute in CYMBALTA-treated patients, decrease of 0.17 beats per minute in placebo-treated patients).

Laboratory Changes in Adults

CYMBALTA treatment in placebo-controlled clinical trials across approved adult populations, was associated with small mean increases from baseline to endpoint in ALT, AST, CPK, and alkaline phosphatase; infrequent, modest, transient, abnormal values were observed for these analytes in CYMBALTA-treated patients when compared with placebo-treated patients [see Warnings and Precautions (5.2)]. High bicarbonate, cholesterol, and abnormal (high or low) potassium, were observed more frequently in CYMBALTA-treated patients compared to placebo-treated patients.

Other Adverse Reactions Observed During the Clinical Trial Evaluation of CYMBALTA in Adults

Following is a list of adverse reactions reported by patients treated with CYMBALTA in clinical adult trials. In clinical trials of all approved adult populations, 34,756 patients were treated with CYMBALTA. Of these, 27% (9337) took CYMBALTA for at least 6 months, and 12% (4317) took CYMBALTA for at least one year. The following listing is not intended to include reactions (1) already listed in previous tables or elsewhere in labeling, (2) for which a drug cause was remote, (3) which were so general as to be uninformative, (4) which were not considered to have significant clinical implications, or (5) which occurred at a rate equal to or less than placebo.

Reactions are categorized by body system according to the following definitions: frequent adverse reactions are those occurring in at least 1/100 patients; infrequent adverse reactions are those occurring in 1/100 to 1/1000 patients; rare reactions are those occurring in fewer than 1/1000 patients.

- Cardiac Disorders — Frequent: palpitations; Infrequent: myocardial infarction, tachycardia, and Takotsubo cardiomyopathy.
- Ear and Labyrinth Disorders — Frequent: vertigo; Infrequent: ear pain and tinnitus.
- Endocrine Disorders — Infrequent: hypothyroidism.
- Eye Disorders — Frequent: vision blurred; Infrequent: diplopia, dry eye, and visual impairment.
- Gastrointestinal Disorders — Frequent: flatulence; Infrequent: dysphagia, eructation, gastritis, gastrointestinal hemorrhage, halitosis, and stomatitis; Rare: gastric ulcer.
- General Disorders and Administration Site Conditions — Frequent: chills/rigors; Infrequent: falls, feeling abnormal, feeling hot and/or cold, malaise, and thirst; Rare: gait disturbance.
- Infections and Infestations — Infrequent: gastroenteritis and laryngitis.
- Investigations — Frequent: weight increased, weight decreased; Infrequent: blood cholesterol increased.
- Metabolism and Nutrition Disorders — Infrequent: dehydration and hyperlipidemia; Rare: dyslipidemia.
- Musculoskeletal and Connective Tissue Disorders — Frequent: musculoskeletal pain; Infrequent: muscle tightness and muscle twitching.
- Nervous System Disorders — Frequent: dysgeusia, lethargy, and paraesthesia/hypoesthesia; Infrequent: disturbance in attention, dyskinesia, myoclonus, and poor quality sleep; Rare: dysarthria.
- Psychiatric Disorders — Frequent: abnormal dreams and sleep disorder; Infrequent: apathy, bruxism, disorientation/confusional state, irritability, mood swings, and suicide attempt; Rare: completed suicide.
- Renal and Urinary Disorders — Frequent: urinary frequency; Infrequent: dysuria, micturition urgency, nocturia, polyuria, and urine odor abnormal.
- Reproductive System and Breast Disorders — Frequent: anorgasmia/orgasm abnormal; Infrequent: menopausal symptoms, sexual dysfunction, and testicular pain; Rare: menstrual disorder.
- Respiratory, Thoracic and Mediastinal Disorders — Frequent: yawning, oropharyngeal pain; Infrequent: throat tightness.
- Skin and Subcutaneous Tissue Disorders — Frequent: pruritus; Infrequent: cold sweat, dermatitis contact, erythema, increased tendency to bruise, night sweats, and photosensitivity reaction; Rare: ecchymosis.
- Vascular Disorders — Frequent: hot flush; Infrequent: flushing, orthostatic hypotension, and peripheral coldness.

Adverse Reactions Observed in Placebo-Controlled Clinical Trials in Pediatric Patients

Pediatric Clinical Trial Database

The data described below reflect exposure to CYMBALTA (N=567) in pediatric patients aged 7 to 18 years of age from two 10-week, placebo-controlled trials in patients with MDD (N=341) (Studies MDD-6 and MDD-7), one 10-week placebo-controlled trial in GAD (N=135) (Study GAD-6), and a 13-week trial in fibromyalgia (N=91). CYMBALTA is not approved for the treatment of MDD in pediatric patients [see Use in Specific Populations (8.4)]. Of the CYMBALTA-treated patients in these studies, 36% were 7 to 11 years of age (64% were between 12 to 18 years old), 55% were female, and 69% were Caucasian. Patients received 30 to 120 mg of CYMBALTA per day during placebo-controlled acute treatment studies. In the pediatric MDD, GAD, and fibromyalgia trials up to 40 weeks long, there were 988 CYMBALTA-treated pediatric patients aged 7 to 17 years of age (most patients received 30-120 mg per day) – 35% were 7 to 11 years of age (65% were 12 to 17 years old) and 56% were female.

Most Common Adverse Reactions in Pediatric Trials

The most common adverse reactions (≥5% in CYMBALTA-treated patients and at least twice the incidence of placebo-treated patients) in all pooled pediatric populations (MDD, GAD, and fibromyalgia) were decreased weight, decreased appetite, nausea, vomiting, fatigue, and diarrhea.

Adverse Reactions in Pediatric Patients Aged 7 to 17 Years Old with MDD and GAD

The adverse reaction profile observed in clinical trials in pediatric patients aged 7 to 18 years old with MDD and GAD was consistent with the adverse reaction profile observed in adult clinical trials. The most common (≥5% and twice placebo) adverse reactions observed in these pediatric clinical trials included: nausea, diarrhea, decreased weight, and dizziness.

Table 6 provides the incidence of adverse reactions in MDD and GAD pediatric placebo-controlled trials that occurred in greater than 2% of patients treated with CYMBALTA and with an incidence greater than patients treated with placebo. CYMBALTA is not approved in the treatment of MDD in pediatric patients [see Use in Specific Populations (8.4)].

Table 6: Adverse Reactions: Incidence of 2% or More and Greater than Placebo in Three 10-week Pediatric Placebo-Controlled Trials in MDD and GADa
System Organ Class/Adverse Reaction | Percentage of Pediatric Patients Reporting Reaction
System Organ Class/Adverse Reaction | CYMBALTA (N=476) | Placebo (N=362)
Gastrointestinal Disorders
Nausea | 18 | 8
Abdominal Painb | 13 | 10
Vomiting | 9 | 4
Diarrhea | 6 | 3
Dry Mouth | 2 | 1
General Disorders and Administration Site Conditions
Fatiguec | 7 | 5
Investigations
Decreased Weightd | 14 | 6
Metabolism and Nutrition Disorders
Decreased Appetite | 10 | 5
Nervous System Disorders
Headache | 18 | 13
Somnolencee | 11 | 6
Dizziness | 8 | 4
Psychiatric Disorders
Insomniaf | 7 | 4
Respiratory, Thoracic, and Mediastinal Disorders
Oropharyngeal Pain | 4 | 2
Cough | 3 | 1
a CYMBALTA is not approved for the treatment of pediatric MDD [see Use in Specific Populations (8.4)]. The inclusion of an event in the table is determined based on the percentages before rounding; however, the percentages displayed in the table are rounded to the nearest integer.
b Also includes abdominal pain upper, abdominal pain lower, abdominal tenderness, abdominal discomfort, and gastrointestinal pain.
c Also includes asthenia.
d Frequency based on weight measurement meeting potentially clinically significant threshold of ≥3.5% weight loss (N=467 CYMBALTA; N=354 Placebo).
e Also includes hypersomnia and sedation.
f Also includes initial insomnia, insomnia, middle insomnia, and terminal insomnia.

Other adverse reactions that occurred at an incidence of less than 2% and were reported by more CYMBALTA-treated patients than placebo-treated patients in pediatric MDD and GAD clinical trials included: abnormal dreams (including nightmare), anxiety, flushing (including hot flush), hyperhidrosis, palpitations, pulse increased, and tremor (CYMBALTA is not approved to treat pediatric patients with MDD).

The most commonly reported symptoms following discontinuation of CYMBALTA in pediatric MDD and GAD clinical trials included headache, dizziness, insomnia, and abdominal pain [see Warnings and Precautions (5.7)].

Growth (Height and Weight) in Pediatric Patients 7 to 17 Years Old with GAD and MDD

Decreased appetite and weight loss have been observed in association with the use of SSRIs and SNRIs. CYMBALTA-treated pediatric patients in clinical trials experienced a 0.1 kg mean decrease in weight at 10 weeks, compared with a mean weight gain of approximately 0.9 kg in placebo-treated pediatric patients. The proportion of patients who experienced a clinically significant decrease in weight (≥3.5%) was greater in the CYMBALTA group than in the placebo group (16% and 6%, respectively). Subsequently, over the 4- to 6-month uncontrolled extension periods, CYMBALTA-treated patients on average trended toward recovery to their expected baseline weight percentile based on population data from age- and sex-matched peers.

In studies up to 9 months, CYMBALTA-treated pediatric patients experienced an increase in height of 1.7 cm on average (2.2 cm increase in patients 7 to 11 years of age and 1.3 cm increase in patients 12 to 17 years of age). While height increase was observed during these studies, a mean decrease of 1% in height percentile was observed (decrease of 2% in patients 7 to 11 years of age and increase of 0.3% in patients 12 to 17 years of age). Weight and height should be monitored regularly in pediatric patients treated with CYMBALTA [see Use in Specific Populations (8.4)].

Adverse Reactions in Pediatric Patients Aged 13 to 17 Years Old with Fibromyalgia

Table 7 provides the incidence of adverse reactions in a fibromyalgia pediatric placebo-controlled trial (Study FM-4) that occurred in greater than 5% of patients treated with CYMBALTA and with an incidence greater than patients treated with placebo [see Clinical Studies (14.5)].

Table 7: Adverse Reactions: Incidence of 5% or More and Greater than Placebo in a 13-week Placebo-Controlled Trial in Pediatric Patients 13 to 17 Years Old with Fibromyalgia (Study FM-4)a
 | CYMBALTA (N=91) | Placebo (N=93)
Nausea | 25% | 15%
Decreased appetite | 15% | 3%
Vomiting | 15% | 5%
Decreased weightb | 15% | 5%
Headache | 14% | 11%
Nasopharyngitis | 9% | 2%
Somnolence | 9% | 3%
Upper respiratory tract infection | 7% | 2%
Viral gastroenteritis | 5% | 0%
Fatigue | 5% | 2%
a The inclusion of an event in the table is determined based on the percentages before rounding; however, the percentages displayed in the table are rounded to the nearest integer.
b Frequency based on weight measurement meeting potentially clinically significant threshold of ≥3.5% weight loss (N=89 CYMBALTA; N=92 Placebo).

6.2 Postmarketing Experience

The following adverse reactions have been identified during post approval use of CYMBALTA. Because these reactions are reported voluntarily from a population of uncertain size, it is not always possible to reliably estimate their frequency or establish a causal relationship to drug exposure.

Adverse reactions reported since market introduction that were temporally related to CYMBALTA therapy and not mentioned elsewhere in labeling include: acute pancreatitis, anaphylactic reaction, aggression and anger (particularly early in treatment or after treatment discontinuation), angioneurotic edema, angle-closure glaucoma, colitis (microscopic or unspecified), cutaneous vasculitis (sometimes associated with systemic involvement), extrapyramidal disorder, galactorrhea, gynecological bleeding, hallucinations, hyperglycemia, hyperprolactinemia, hypersensitivity, hypertensive crisis, muscle spasm, rash, restless legs syndrome, seizures upon treatment discontinuation, supraventricular arrhythmia, tinnitus (upon treatment discontinuation), trismus, and urticaria.

7 DRUG INTERACTIONS

Both CYP1A2 and CYP2D6 are responsible for duloxetine metabolism.

7.1 Inhibitors of CYP1A2

When CYMBALTA 60 mg was co-administered with fluvoxamine 100 mg, a potent CYP1A2 inhibitor, to male subjects (n=14) duloxetine AUC was increased approximately 6-fold, the Cmax was increased about 2.5-fold, and duloxetine t1/2 was increased approximately 3-fold. Other drugs that inhibit CYP1A2 metabolism include cimetidine and quinolone antimicrobials such as ciprofloxacin and enoxacin [see Warnings and Precautions (5.12)].

7.2 Inhibitors of CYP2D6

Concomitant use of CYMBALTA (40 mg once daily) with paroxetine (20 mg once daily) increased the concentration of duloxetine AUC by about 60%, and greater degrees of inhibition are expected with higher doses of paroxetine. Similar effects would be expected with other potent CYP2D6 inhibitors (e.g., fluoxetine, quinidine) [see Warnings and Precautions (5.12)].

7.3 Dual Inhibition of CYP1A2 and CYP2D6

Concomitant administration of CYMBALTA 40 mg twice daily with fluvoxamine 100 mg, a potent CYP1A2 inhibitor, to CYP2D6 poor metabolizer subjects (n=14) resulted in a 6-fold increase in duloxetine AUC and Cmax.

7.4 Drugs that Interfere with Hemostasis (e.g., NSAIDs, Aspirin, and Warfarin)

Serotonin release by platelets plays an important role in hemostasis. Epidemiological studies of the case-control and cohort design that have demonstrated an association between use of psychotropic drugs that interfere with serotonin reuptake and the occurrence of upper gastrointestinal bleeding have also shown that concurrent use of an NSAID or aspirin may potentiate this risk of bleeding. Altered anticoagulant effects, including increased bleeding, have been reported when SSRIs or SNRIs are co-administered with warfarin. Concomitant administration of warfarin (2-9 mg once daily) under steady state conditions with CYMBALTA 60 or 120 mg once daily for up to 14 days in healthy subjects (n=15) did not significantly change INR from baseline (mean INR changes ranged from 0.05 to +0.07). The total warfarin (protein bound plus free drug) pharmacokinetics (AUCτ,ss, Cmax,ss or tmax,ss) for both R- and S-warfarin were not altered by duloxetine. Because of the potential effect of duloxetine on platelets, patients receiving warfarin therapy should be carefully monitored when CYMBALTA is initiated or discontinued [see Warnings and Precautions (5.5)].

7.5 Lorazepam

Under steady-state conditions for CYMBALTA (60 mg Q 12 hours) and lorazepam (2 mg Q 12 hours), the pharmacokinetics of duloxetine were not affected by co-administration.

7.6 Temazepam

Under steady-state conditions for CYMBALTA (20 mg qhs) and temazepam (30 mg qhs), the pharmacokinetics of duloxetine were not affected by co-administration.

7.7 Drugs that Affect Gastric Acidity

CYMBALTA has an enteric coating that resists dissolution until reaching a segment of the gastrointestinal tract where the pH exceeds 5.5. In extremely acidic conditions, CYMBALTA, unprotected by the enteric coating, may undergo hydrolysis to form naphthol. Caution is advised in using CYMBALTA in patients with conditions that may slow gastric emptying (e.g., some diabetics). Drugs that raise the gastrointestinal pH may lead to an earlier release of duloxetine. However, co-administration of CYMBALTA with aluminum- and magnesium-containing antacids (51 mEq) or CYMBALTA with famotidine, had no significant effect on the rate or extent of duloxetine absorption after administration of a 40 mg oral dose. It is unknown whether the concomitant administration of proton pump inhibitors affects duloxetine absorption [see Warnings and Precautions (5.14)].

7.8 Drugs Metabolized by CYP1A2

In vitro drug interaction studies demonstrate that duloxetine does not induce CYP1A2 activity. Therefore, an increase in the metabolism of CYP1A2 substrates (e.g., theophylline, caffeine) resulting from induction is not anticipated, although clinical studies of induction have not been performed. Duloxetine is an inhibitor of the CYP1A2 isoform in in vitro studies, and in two clinical studies the average (90% confidence interval) increase in theophylline AUC was 7% (1%-15%) and 20% (13%-27%) when co-administered with CYMBALTA (60 mg twice daily).

7.9 Drugs Metabolized by CYP2D6

Duloxetine is a moderate inhibitor of CYP2D6. When CYMBALTA was administered (at a dose of 60 mg twice daily) in conjunction with a single 50 mg dose of desipramine, a CYP2D6 substrate, the AUC of desipramine increased 3-fold [see Warnings and Precautions (5.12)].

7.10 Drugs Metabolized by CYP2C9

Results of in vitro studies demonstrate that duloxetine does not inhibit activity. In a clinical study, the pharmacokinetics of S-warfarin, a CYP2C9 substrate, were not significantly affected by duloxetine [see Drug Interactions (7.4)].

7.11 Drugs Metabolized by CYP3A

Results of in vitro studies demonstrate that duloxetine does not inhibit or induce CYP3A activity. Therefore, an increase or decrease in the metabolism of CYP3A substrates (e.g., oral contraceptives and other steroidal agents) resulting from induction or inhibition is not anticipated, although clinical studies have not been performed.

7.12 Drugs Metabolized by CYP2C19

Results of in vitro studies demonstrate that duloxetine does not inhibit CYP2C19 activity at therapeutic concentrations. Inhibition of the metabolism of CYP2C19 substrates is therefore not anticipated, although clinical studies have not been performed.

7.13 Monoamine Oxidase Inhibitors (MAOIs)

[See Dosage and Administration (2.9, 2.10), Contraindications (4), and Warnings and Precautions (5.4)].

7.14 Other Serotonergic Drugs

The concomitant use of serotonergic drugs (including other SNRIs, SSRIs, triptans, tricyclic antidepressants, opioids, lithium, buspirone, amphetamines, tryptophan, and St. John's Wort) with CYMBALTA increases the risk of serotonin syndrome. Monitor patients for signs and symptoms of serotonin syndrome, particularly during treatment initiation and dosage increases. If serotonin syndrome occurs, consider discontinuation of CYMBALTA and/or concomitant serotonergic drugs [see Warnings and Precautions (5.4)].

7.15 Alcohol

When CYMBALTA and ethanol were administered several hours apart so that peak concentrations of each would coincide, CYMBALTA did not increase the impairment of mental and motor skills caused by alcohol.

In the CYMBALTA clinical trials database, three CYMBALTA-treated patients had liver injury as manifested by ALT and total bilirubin elevations, with evidence of obstruction. Substantial intercurrent ethanol use was present in each of these cases, and this may have contributed to the abnormalities seen [see Warnings and Precautions (5.2, 5.12)].

7.16 CNS Drugs

[See Warnings and Precautions (5.12)].

7.17 Drugs Highly Bound to Plasma Protein

Because duloxetine is highly bound to plasma protein, administration of CYMBALTA to a patient taking another drug that is highly protein bound may cause increased free concentrations of the other drug, potentially resulting in adverse reactions. However, co-administration of CYMBALTA (60 or 120 mg) with warfarin (2-9 mg), a highly protein-bound drug, did not result in significant changes in INR and in the pharmacokinetics of either total S-or total R-warfarin (protein bound plus free drug) [see Drug Interactions (7.4)].

8 USE IN SPECIFIC POPULATIONS

8.1 Pregnancy

Pregnancy Exposure Registry

There is a pregnancy exposure registry that monitors the pregnancy outcomes in women exposed to antidepressants, including CYMBALTA, during pregnancy. Healthcare providers are encouraged to register patients by contacting the National Pregnancy Registry for Antidepressants at 1-866-961-2388 or online at
https://womensmentalhealth.org/research/pregnancyregistry/.

Risk Summary

Data from a postmarketing retrospective cohort study indicate that use of duloxetine in the month before delivery may be associated with an increased risk of postpartum hemorrhage. Data from published literature and from a postmarketing retrospective cohort study have not identified a clear drug-associated risk of major birth defects or other adverse developmental outcomes (see Data). There are risks associated with untreated depression and fibromyalgia in pregnancy, and with exposure to SNRIs and SSRIs, including CYMBALTA, during pregnancy (see Clinical Considerations).

In rats and rabbits treated with duloxetine during the period of organogenesis, fetal weights were decreased but there was no evidence of developmental effects at doses up to 3 and 6 times, respectively, the maximum recommended human dose (MRHD) of 120 mg/day given to adolescents on a mg/m^2 basis. When duloxetine was administered orally to pregnant rats throughout gestation and lactation, pup weights at birth and pup survival to 1 day postpartum were decreased at a dose 2 times the MRHD given to adolescents on a mg/m^2 basis. At this dose, pup behaviors consistent with increased reactivity, such as increased startle response to noise and decreased habituation of locomotor activity were observed. Post-weaning growth was not adversely affected.

The estimated background risk of major birth defects and miscarriage for the indicated population is unknown. All pregnancies have a background risk of birth defect, loss, or other adverse outcomes. In the U.S. general population, the estimated background risk of major birth defects and miscarriage in clinically recognized pregnancies is 2 to 4% and 15 to 20%, respectively.

Clinical Considerations

Disease-associated Maternal and/or Embryo/Fetal Risk

Women who discontinue antidepressants during pregnancy are more likely to experience a relapse of major depression than women who continue antidepressants. This finding is from a prospective, longitudinal study that followed 201 pregnant women with a history of major depressive disorder who were euthymic and taking antidepressants at the beginning of pregnancy. Consider the risk of untreated depression when discontinuing or changing treatment with antidepressant medication during pregnancy and postpartum.

Pregnant women with fibromyalgia are at increased risk for adverse maternal and infant outcomes including preterm premature rupture of membranes, preterm birth, small for gestational age, intrauterine growth restriction, placental disruption, and venous thrombosis. It is not known if these adverse maternal and fetal outcomes are a direct result of fibromyalgia or other comorbid factors.

Maternal Adverse Reactions

Use of CYMBALTA in the month before delivery may be associated with an increased risk of postpartum hemorrhage [see Warnings and Precautions (5.5)].

Fetal/Neonatal Adverse Reaction

Neonates exposed to CYMBALTA and other SNRIs or SSRIs late in the third trimester have developed complications requiring prolonged hospitalization, respiratory support, and tube feeding. Such complications can arise immediately upon delivery. Reported clinical findings have included respiratory distress, cyanosis, apnea, seizures, temperature instability, feeding difficulty, vomiting, hypoglycemia, hypotonia, hypertonia, hyperreflexia, tremor, jitteriness, irritability, and constant crying. These findings are consistent with either a direct toxic effect of the SNRIs or SSRIs, or possibly, a drug discontinuation syndrome. It should be noted that, in some cases, the clinical picture is consistent with serotonin syndrome [see Warnings and Precautions (5.4)].

Data

Human Data

Data from a postmarketing retrospective claims-based cohort study found an increased risk for postpartum hemorrhage among 955 pregnant women exposed to duloxetine in the last month of pregnancy compared to 4,128,460 unexposed pregnant women (adjusted relative risk: 1.53; 95% CI: 1.08-2.18). The same study did not find a clinically meaningful increase in the risk for major birth defects in the comparison of 2532 women exposed to duloxetine in the first trimester of pregnancy to 1,284,827 unexposed women after adjusting for several confounders. Methodologic limitations include possible residual confounding, misclassification of exposure and outcomes, lack of direct measures of disease severity, and lack of information about alcohol use, nutrition, and over-the-counter medication exposures.

Animal Data

In animal reproduction studies, duloxetine has been shown to have adverse effects on embryo/fetal and postnatal development.

When duloxetine was administered orally to pregnant rats and rabbits during the period of organogenesis, there was no evidence of malformations or developmental variations at doses up to 45 mg/kg/day [3 and 6 times, respectively, the MRHD of 120 mg/day given to adolescents on a mg/m^2 basis]. However, fetal weights were decreased at this dose, with a no-effect dose of 10 mg/kg/day (approximately equal to the MRHD in rats and 2 times the MRHD in rabbits).

When duloxetine was administered orally to pregnant rats throughout gestation and lactation, the survival of pups to 1 day postpartum and pup body weights at birth and during the lactation period were decreased at a dose of 30 mg/kg/day (2 times the MRHD given to adolescents on a mg/m^2 basis); the no-effect dose was 10 mg/kg/day. Furthermore, behaviors consistent with increased reactivity, such as increased startle response to noise and decreased habituation of locomotor activity, were observed in pups following maternal exposure to 30 mg/kg/day. Post-weaning growth and reproductive performance of the progeny were not affected adversely by maternal duloxetine treatment.

8.2 Lactation

Risk Summary

Data from published literature report the presence of duloxetine in human milk (see Data). There are reports of sedation, poor feeding, and poor weight gain in infants exposed to duloxetine through breast milk (see Clinical Considerations). There are no data on the effect of duloxetine on milk production.

The developmental and health benefits of breastfeeding should be considered along with the mother's clinical need for CYMBALTA and any potential adverse effects on the breastfed child from CYMBALTA or from the underlying maternal condition.

Clinical Considerations

Infants exposed to CYMBALTA should be monitored for sedation, poor feeding and poor weight gain.

Data

Disposition of CYMBALTA was studied in 6 lactating women who were at least 12 weeks postpartum and had elected to wean their infants. The women were given 40 mg of CYMBALTA twice daily for 3.5 days. The peak concentration measured in breast milk occurred at a median of 3 hours after the dose. The amount of CYMBALTA in breast milk was approximately 7 mcg/day while on that dose; the estimated daily infant dose was approximately 2 mcg/kg/day, which is less than 1% of the maternal dose. The presence of CYMBALTA metabolites in breast milk was not examined.

8.4 Pediatric Use

The safety and effectiveness of CYMBALTA have been established for treatment of generalized anxiety disorder (GAD) in patients 7 to 17 years of age and for treatment of juvenile fibromyalgia syndrome in patients 13 to 17 years of age. The safety and effectiveness of CYMBALTA have not been established in pediatric patients with major depressive disorder (MDD), diabetic peripheral neuropathic pain, or chronic musculoskeletal pain.

Antidepressants increased the risk of suicidal thoughts and behavior in pediatric patients. Monitor all pediatric patients being treated with antidepressants for clinical worsening and emergence of suicidal thoughts and behaviors, especially during the initial few months of treatment, or at times of dosage changes [see Warnings and Precautions (5.1)]. Perform regular monitoring of weight and growth in pediatric patients treated with CYMBALTA [see Adverse Reactions (6.1)].

Generalized Anxiety Disorder

Use of CYMBALTA for the treatment of GAD in patients 7 to 17 years of age is supported by one 10-week, placebo-controlled trial (GAD-6). The study included 272 pediatric patients with GAD of which 47% were 7 to 11 years of age (53% were 12 to 17 years of age). CYMBALTA demonstrated superiority over placebo as measured by greater improvement in the Pediatric Anxiety Rating Scale (PARS) for GAD severity score [see Clinical Studies (14.3)].

The safety and effectiveness of CYMBALTA for the treatment of GAD in pediatric patients less than 7 years of age have not been established.

Fibromyalgia

Use of CYMBALTA for treatment of fibromyalgia in patients 13 to 17 years of age is supported by a 13-week placebo-controlled trial in 184 patients with juvenile fibromyalgia syndrome (Study FM-4). CYMBALTA showed improvement over placebo on the primary endpoint, change from baseline to end-of-treatment on the Brief Pain Inventory (BPI) – Modified Short Form: Adolescent Version 24-hour average pain severity rating [see Clinical Studies (14.5)].

The safety and effectiveness of CYMBALTA for the treatment of fibromyalgia in patients less than 13 years of age have not been established.

Major Depressive Disorder

The safety and effectiveness of CYMBALTA have not been established in pediatric patients for the treatment of MDD. Efficacy of CYMBALTA was not demonstrated in two 10-week, placebo-controlled trials with 800 pediatric patients aged 7 to 17 years old with MDD (MDD-6 and MDD-7). Neither CYMBALTA nor an active control (approved for treatment of pediatric MDD) was superior to placebo.

The most frequently observed adverse reactions in the MDD pediatric clinical trials included nausea, headache, decreased weight, and abdominal pain. Decreased appetite and weight loss have been observed in association with the use of SSRIs and SNRIs.

Juvenile Animal Toxicology Data

Duloxetine administration to young rats from post-natal day 21 (weaning) through post-natal day 90 (adult) resulted in decreased body weights that persisted into adulthood, but recovered when drug treatment was discontinued; slightly delayed (~1.5 days) sexual maturation in females, without any effect on fertility; and a delay in learning a complex task in adulthood, which was not observed after drug treatment was discontinued. These effects were observed at the high dose of 45 mg/kg/day (2 times the MRHD, for a child); the no-effect-level was 20 mg/kg/day (≈1 times the MRHD, for a child).

8.5 Geriatric Use

Geriatric Exposure in Premarketing Clinical Trials of CYMBALTA

- Of the 2,418 patients in MDD trials, 6% (143) were 65 years of age or over.
- Of the 1041 patients in CLBP trials, 21% (221) were 65 years of age or over.
- Of the 487 patients in OA trials, 41% (197) were 65 years of age or over.
- Of the 1,074 patients in the DPNP trials, 33% (357) were 65 years of age or over.
- Of the 1,761 patients in FM trials, 8% (140) were 65 years of age or over.

In the MDD, GAD, DPNP, FM, OA, and CLBP studies, no overall differences in safety or effectiveness were generally observed between these patients and younger adult patients, and other reported clinical experience has not identified differences in responses between these geriatric and younger adult patients, but greater sensitivity of some older patients cannot be ruled out.

SSRIs and SNRIs, including CYMBALTA have been associated with clinically significant hyponatremia in geriatric patients, who may be at greater risk for this adverse reaction [see Warnings and Precautions (5.13)].

In an analysis of data from all placebo-controlled-trials, CYMBALTA-treated patients reported a higher rate of falls compared to placebo-treated patients. The increased risk appears to be proportional to a patient's underlying risk for falls. Underlying risk appears to increase steadily with age. As geriatric patients tend to have a higher prevalence of risk factors for falls such as medications, medical comorbidities and gait disturbances, the impact of increasing age by itself on falls during CYMBALTA treatment is unclear. Falls with serious consequences including bone fractures and hospitalizations have been reported with CYMBALTA use [see Warnings and Precautions (5.3) and Adverse Reactions (6.1)].

The pharmacokinetics of duloxetine after a single dose of 40 mg were compared in healthy elderly females (65 to 77 years) and healthy middle-age females (32 to 50 years). There was no difference in the Cmax, but the AUC of duloxetine was somewhat (about 25%) higher and the half-life about 4 hours longer in the elderly females. Population pharmacokinetic analyses suggest that the typical values for clearance decrease by approximately 1% for each year of age between 25 to 75 years of age; but age as a predictive factor only accounts for a small percentage of between-patient variability. Dosage adjustment based on the age of the adult patient is not necessary.

8.6 Gender

Duloxetine's half-life is similar in men and women. Dosage adjustment based on gender is not necessary.

8.7 Smoking Status

Duloxetine bioavailability (AUC) appears to be reduced by about one-third in smokers. Dosage modifications are not recommended for smokers.

8.8 Race

No specific pharmacokinetic study was conducted to investigate the effects of race.

8.9 Hepatic Impairment

Patients with clinically evident hepatic impairment have decreased duloxetine metabolism and elimination. After a single 20 mg dose of CYMBALTA, 6 cirrhotic patients with moderate liver impairment (Child-Pugh Class B) had a mean plasma duloxetine clearance about 15% that of age- and gender-matched healthy subjects, with a 5-fold increase in mean exposure (AUC). Although Cmax was similar to normals in the cirrhotic patients, the half-life was about 3 times longer [see Dosage and Administration (2.7) and Warnings and Precautions (5.14)].

8.10 Severe Renal Impairment

Limited data are available on the effects of CYMBALTA in patients with end-stage renal disease (ESRD). After a single 60 mg dose of CYMBALTA, Cmax and AUC values were approximately 100% greater in patients with ESRD receiving chronic intermittent hemodialysis than in subjects with normal renal function. The elimination half-life, however, was similar in both groups. The AUCs of the major circulating metabolites, 4-hydroxy duloxetine glucuronide and 5-hydroxy, 6-methoxy duloxetine sulfate, largely excreted in urine, were approximately 7- to 9-fold higher and would be expected to increase further with multiple dosing. Population PK analyses suggest that mild to moderate degrees of renal impairment (estimated CrCl 30-80 mL/min) have no significant effect on duloxetine apparent clearance [see Dosage and Administration (2.7) and Warnings and Precautions (5.14)].

9 DRUG ABUSE AND DEPENDENCE

9.2 Abuse

In animal studies, duloxetine did not demonstrate barbiturate-like (depressant) abuse potential.

While CYMBALTA has not been systematically studied in humans for its potential for abuse, there was no indication of drug-seeking behavior in the clinical trials. However, it is not possible to predict on the basis of premarketing experience the extent to which a CNS active drug will be misused, diverted, and/or abused once marketed. Consequently, physicians should carefully evaluate patients for a history of drug abuse and follow such patients closely, observing them for signs of misuse or abuse of CYMBALTA (e.g., development of tolerance, incrementation of dose, drug-seeking behavior).

9.3 Dependence

In drug dependence studies, duloxetine did not demonstrate dependence-producing potential in rats.

10 OVERDOSAGE

10.1 Signs and Symptoms

In postmarketing experience, fatal outcomes have been reported for acute CYMBALTA overdoses, primarily with mixed overdoses, but also with CYMBALTA only, including 1000 mg of CYMBALTA (approximately 8.3 times the maximum recommended dosage). Signs and symptoms of overdose (CYMBALTA alone or with mixed drugs) included somnolence, coma, serotonin syndrome, seizures, syncope, tachycardia, hypotension, hypertension, and vomiting.

10.2 Management of Overdose

There is no specific antidote to a CYMBALTA overdosage, but if serotonin syndrome ensues, specific treatment (such as with cyproheptadine and/or temperature control) may be considered.

In case of acute overdose with CYMBALTA, treatment should consist of those general measures employed in the management of overdose with any drug, such as assuring an adequate airway, oxygenation, and ventilation and monitoring cardiac rhythm and vital signs. Gastric lavage with a large-bore orogastric tube with appropriate airway protection, if needed, may be indicated if performed soon after ingestion or in symptomatic patients. Induction of emesis is not recommended.

Activated charcoal may be useful in limiting absorption of duloxetine from the gastrointestinal tract. Administration of activated charcoal has been shown to decrease duloxetine AUC and Cmax by an average of one-third, although some patients had a limited effect of activated charcoal. Due to the large volume of distribution of duloxetine, forced diuresis, dialysis, hemoperfusion, and exchange transfusion are unlikely to be beneficial.

In managing overdose, the possibility of multiple drug involvement should be considered. A specific caution involves patients who overdose with CYMBALTA and tricyclic antidepressants. In such a case, decreased clearance of the parent tricyclic and/or its active metabolite may increase the possibility of clinically significant sequelae and extend the time needed for close medical observation [see Warnings and Precautions (5.4) and Drug Interactions (7)].

Consider contacting a poison control center (1-800-222-1222 or www.poison.org) for additional information on the treatment of overdosage.

11 DESCRIPTION

CYMBALTA® (duloxetine delayed-release capsules) is a selective serotonin and norepinephrine reuptake inhibitor (SNRI) for oral administration. Its chemical designation is (+)-(S)-N-methyl-γ-(1-naphthyloxy)-2-thiophenepropylamine hydrochloride. The empirical formula is C18H19NOS•HCl, which corresponds to a molecular weight of 333.88. The structural formula is:

Duloxetine hydrochloride is a white to slightly brownish white solid, which is slightly soluble in water.

Each capsule contains enteric-coated pellets of 20, 30, or 60 mg of duloxetine (equivalent to 22.4, 33.7, or 67.3 mg of duloxetine hydrochloride, respectively). These enteric-coated pellets are designed to prevent degradation of the drug in the acidic environment of the stomach. Inactive ingredients include FD&C Blue No. 2, gelatin, hypromellose, hydroxypropyl methylcellulose acetate succinate, sodium lauryl sulfate, sucrose, sugar spheres, talc, titanium dioxide, and triethyl citrate. The 20 and 60 mg capsules also contain iron oxide yellow.

12 CLINICAL PHARMACOLOGY

12.1 Mechanism of Action

Although the exact mechanisms of the antidepressant, central pain inhibitory and anxiolytic actions of duloxetine in humans are unknown, these actions are believed to be related to its potentiation of serotonergic and noradrenergic activity in the CNS.

12.2 Pharmacodynamics

Preclinical studies have shown that duloxetine is a potent inhibitor of neuronal serotonin and norepinephrine reuptake and a less potent inhibitor of dopamine reuptake. Duloxetine has no significant affinity for dopaminergic, adrenergic, cholinergic, histaminergic, opioid, glutamate, and GABA receptors in vitro. Duloxetine does not inhibit monoamine oxidase (MAO).

CYMBALTA is in a class of drugs known to affect urethral resistance [see Warnings and Precautions (5.15)].

Cardiac Electrophysiology

The effect of CYMBALTA 160 mg and 200 mg administered twice daily (2.7 and 3.3 times the maximum recommended dosage, respectively) to steady state was evaluated in a randomized, double-blinded, two-way crossover study in 117 healthy female adult subjects. No QT interval prolongation was detected. CYMBALTA appears to be associated with concentration-dependent but not clinically meaningful QT shortening.

12.3 Pharmacokinetics

Duloxetine has an elimination half-life of about 12 hours (range 8 to 17 hours) and its pharmacokinetics are dose proportional over the therapeutic range. Steady-state plasma concentrations are typically achieved after 3 days of dosing. Elimination of duloxetine is mainly through hepatic metabolism involving two P450 isozymes, CYP1A2 and CYP2D6.

Absorption

After oral CYMBALTA administration, duloxetine hydrochloride is well absorbed. There is a median 2 hour lag until absorption begins (Tlag), with maximal plasma concentrations (Cmax) of duloxetine occurring 6 hours post dose. There is a 3 hour delay in absorption and a one-third increase in apparent clearance of duloxetine after an evening dose as compared to a morning dose.

Effect of Food: Food does not affect the Cmax of duloxetine, but delays the time to reach peak concentration from 6 to 10 hours and it marginally decreases the extent of absorption (AUC) by about 10%.

Distribution

The apparent volume of distribution averages about 1640 L. Duloxetine is highly bound (>90%) to proteins in human plasma, binding primarily to albumin and α1-acid glycoprotein. The interaction between duloxetine and other highly protein bound drugs has not been fully evaluated. Plasma protein binding of duloxetine is not affected by renal or hepatic impairment.

Elimination

Metabolism

Biotransformation and disposition of duloxetine in humans have been determined following oral administration of ^14C-labeled duloxetine. Duloxetine comprises about 3% of the total radiolabeled material in the plasma, indicating that it undergoes extensive metabolism to numerous metabolites. The major biotransformation pathways for duloxetine involve oxidation of the naphthyl ring followed by conjugation and further oxidation. Both CYP1A2 and CYP2D6 catalyze the oxidation of the naphthyl ring in vitro. Metabolites found in plasma include 4-hydroxy duloxetine glucuronide and 5-hydroxy, 6-methoxy duloxetine sulfate.

Excretion

Many additional metabolites have been identified in urine, some representing only minor pathways of elimination. Only trace (<1% of the dose) amounts of unchanged duloxetine are present in the urine. Most (about 70%) of the duloxetine dose appears in the urine as metabolites of duloxetine; about 20% is excreted in the feces. Duloxetine undergoes extensive metabolism, but the major circulating metabolites have not been shown to contribute significantly to the pharmacologic activity of duloxetine.

Specific Populations

Pediatric Patients

Duloxetine steady-state plasma concentration was comparable in pediatric patients 7 to 17 years of age and adult patients. The average steady-state duloxetine concentration was approximately 30% lower in this pediatric population relative to adult patients. The model-predicted duloxetine steady state plasma concentrations in pediatric patients 7 to 17 years of age were mostly within the concentration range observed in adult patients and did not exceed the concentration range in adults.

13 NONCLINICAL TOXICOLOGY

13.1 Carcinogenesis, Mutagenesis, Impairment of Fertility

Carcinogenesis

Duloxetine was administered in the diet to mice and rats for 2 years.

In female mice receiving duloxetine at 140 mg/kg/day (3 times the maximum recommended human dose (MRHD) of 120 mg/day given to children on a mg/m^2 basis), there was an increased incidence of hepatocellular adenomas and carcinomas. The no-effect dose was 50 mg/kg/day (1 time the MRHD given to children). Tumor incidence was not increased in male mice receiving duloxetine at doses up to 100 mg/kg/day (2 times the MRHD given to children).

In rats, dietary doses of duloxetine up to 27 mg/kg/day in females (1 time the MRHD given to children) and up to 36 mg/kg/day in males (1.4 times the MRHD given to children) did not increase the incidence of tumors.

Mutagenesis

Duloxetine was not mutagenic in the in vitro bacterial reverse mutation assay (Ames test) and was not clastogenic in an in vivo chromosomal aberration test in mouse bone marrow cells. Additionally, duloxetine was not genotoxic in an in vitro mammalian forward gene mutation assay in mouse lymphoma cells or in an in vitro unscheduled DNA synthesis (UDS) assay in primary rat hepatocytes, and did not induce sister chromatid exchange in Chinese hamster bone marrow in vivo.

Impairment of Fertility

Duloxetine administered orally to either male or female rats prior to and throughout mating at doses up to 45 mg/kg/day (3 times the MRHD given to adolescents on a mg/m^2 basis) did not alter mating or fertility.

14 CLINICAL STUDIES

14.1 Overview of the Clinical Trials

The efficacy of CYMBALTA has been established in the following populations in adequate and well-controlled trials:

- Major Depressive Disorder (MDD): 4 short-term (Studies MDD-1, MDD-2, MDD-3, and MDD-4) and 1 maintenance trial (Study MDD-5) in adults [see Clinical Studies (14.2)].
- Generalized Anxiety Disorder (GAD): 3 short-term trials in adults (Studies GAD-1, GAD-2, and GAD-3), 1 maintenance trial in adults (Study GAD-4), 1 short-term trial in geriatric patients (Study GAD-5), and 1 short-term trial in pediatric patients 7 to 17 years of age (Study GAD-6) [see Clinical Studies (14.3)].
- Diabetic Peripheral Neuropathic Pain (DPNP): Two 12-week trials in adults (Studies DPNP-1 and DPNP-2) [see Clinical Studies (14.4)].
- Fibromyalgia (FM): Two trials in adults (one of 3 months duration and one of 6 months duration) (Studies FM-1 and FM-2) and one 13-week trial in pediatric patients 13 to 17 years of age (Study FM-4) [see Clinical Studies (14.5)].
- Chronic Musculoskeletal Pain: Two 12- to 13-week trials in adult patients with chronic low back pain (CLBP) (Studies CLBP-1 and CLBP-3) and one 13-week trial in adult patients with chronic pain due to osteoarthritis (OA) (Study OA-1) [see Clinical Studies (14.6)].

Additionally, a summary of the following trials that did not demonstrate efficacy are presented below: Study FM-3 (a 16- week trial in adult patients with fibromyalgia), Study CLBP-2 (a 13-week trial in adult patients with CLBP), and Study OA-2 (a 13-week trial in adult patients with chronic pain due to OA).

14.2 Major Depressive Disorder in Adults

The efficacy of CYMBALTA as a treatment for MDD in adults was established in 4 randomized, double-blind, placebo-controlled, fixed-dose trials in adult outpatients (18 to 83 years) meeting DSM-IV criteria for MDD:

- In Studies MDD-1 and MDD-2, patients were randomized to CYMBALTA 60 mg once daily (N=123 and N=128, respectively) or placebo (N=122 and N=139, respectively) for 9 weeks
- In Study MDD-3, patients were randomized to CYMBALTA 20 or 40 mg twice daily (N=86 and N=91, respectively) or placebo (N=89) for 8 weeks
- In Study MDD-4, patients were randomized to CYMBALTA 40 or 60 mg twice daily (N=95 and N=93, respectively) or placebo (N=93) for 8 weeks.

In all four trials, CYMBALTA demonstrated superiority over placebo as measured by improvement in the 17-item Hamilton Depression Rating Scale (HAMD-17) total score (see Table 8). There is no evidence that doses greater than 60 mg/day confer additional benefits.

In all of these clinical trials, analyses of the relationship between treatment outcome and age, gender, and race did not suggest any differential responsiveness on the basis of these patient characteristics.

Table 8: Summary of the Primary Efficacy Results for Adult Trials in MDD
Study Number | Treatment Group | Primary Efficacy Measure: HAMD-17
Study Number | Treatment Group | Mean Baseline Score (SD) | LS Mean Change from Baseline (SE) | Placebo-subtracted Differencea (95% CI)
Study MDD-1 | CYMBALTA (60 mg/day)b | 21.5 (4.10) | -10.9 (0.70) | -4.9 (-6.8, -2.9)
 | Placebo | 21.1 (3.71) | -6.1 (0.69) | --
Study MDD-2 | CYMBALTA (60 mg/day)b | 20.3 (3.32) | -10.5 (0.71) | -2.2 (-4.0, -0.3)
 | Placebo | 20.5 (3.42) | -8.3 (0.67) | --
Study MDD-3 | CYMBALTA (20 mg BID)b | 18.6 (5.85) | -7.4 (0.80) | -2.4 (-4.7, -0.2)
 | CYMBALTA (40 mg BID)b | 18.1 (4.52) | -8.6 (0.81) | -3.6 (-5.9, -1.4)
 | Placebo | 17.2 (5.11) | -5.0 (0.81) | --
Study MDD-4 | CYMBALTA (40 mg BID)b | 19.9 (3.54) | -11.0 (0.49) | -2.2 (-3.6, -0.9)
 | CYMBALTA (60 mg BID)b | 20.2 (3.41) | -12.1 (0.49) | -3.3 (-4.7, -1.9)
 | Placebo | 19.9 (3.58) | -8.8 (0.50) | --
SD: standard deviation; SE: standard error; LS Mean: least-squares mean; CI: confidence interval, not adjusted for multiplicity in trials where multiple dose groups were included.
a Difference (drug minus placebo) in least-squares mean change from baseline.
b Doses statistically significantly superior to placebo.

In Study MDD-5, 533 adult patients meeting DSM-IV criteria for MDD received CYMBALTA 60 mg once daily during an initial 12-week open-label treatment phase. Two hundred and seventy-eight patients who responded to open label treatment [defined as meeting the following criteria at weeks 10 and 12: a HAMD-17 total score ≤9, Clinical Global Impressions of Severity (CGI-S) ≤2, and not meeting the DSM-IV criteria for MDD] were randomly assigned to continuation of CYMBALTA at the same dosage (N=136) or to placebo (N=142) for 6 months.

In Study MDD-5, patients on CYMBALTA experienced a statistically significantly longer time to relapse of depression than did patients on placebo (see Figure 1). Relapse was defined as an increase in the CGI-S score of ≥2 points compared with that obtained at week 12, as well as meeting the DSM-IV criteria for MDD at 2 consecutive visits at least 2 weeks apart, where the 2-week temporal criterion had to be satisfied at only the second visit.

Figure 1: Cumulative Proportiona of Adult Patients with MDD Relapse (Study MDD-5)

a Kaplan-Meier estimator method.

14.3 Generalized Anxiety Disorder

GAD Trials in Adults (Including Geriatric Patients)

The efficacy of CYMBALTA in the treatment of generalized anxiety disorder (GAD) was established in 1 fixed-dose randomized, double-blind, placebo-controlled trial and 2 flexible-dose randomized, double-blind, placebo-controlled trials in adult outpatients between 18 and 83 years of age meeting the DSM-IV criteria for GAD (Studies GAD-1, GAD-2, and GAD-3, respectively).

In Studies GAD-1 and GAD-2, the starting dose was 60 mg once daily (down titration to 30 mg once daily was allowed for tolerability reasons; the dosage could be increased to 60 mg once daily). Fifteen percent of patients were down titrated. Study GAD-3 had a starting dose of 30 mg once daily for 1 week before increasing it to 60 mg once daily.

Studies GAD-2 and GAD-3 involved dose titration with CYMBALTA doses ranging from 60 mg once daily to 120 mg once daily (N=168 and N=162) compared to placebo (N=159 and N=161) over a 10-week treatment period. The mean dosage for completers at endpoint in these trials was 104.8 mg/day. Study GAD-1 evaluated CYMBALTA dosages of 60 mg once daily (N=168) and 120 mg once daily (N=170) compared to placebo (N=175) over a 9-week treatment period. While a 120 mg/day dose was shown to be effective, there is no evidence that doses greater than 60 mg/day confer additional benefit.

In all 3 trials, CYMBALTA demonstrated superiority over placebo as measured by greater improvement in the Hamilton Anxiety Scale (HAM-A) total score (see Table 8) and by the Sheehan Disability Scale (SDS) global functional impairment score. The SDS is a composite measurement of the extent emotional symptoms disrupt patient functioning in 3 life domains: work/school, social life/leisure activities, and family life/home responsibilities.

In Study GAD-4, 887 patients meeting DSM-IV-TR criteria for GAD received CYMBALTA 60 mg to 120 mg once daily during an initial 26-week open-label treatment phase. Four hundred and twenty-nine patients who responded to open-label treatment [defined as meeting the following criteria at weeks 24 and 26: a decrease from baseline HAM-A total score by at least 50% to a score no higher than 11, and a Clinical Global Impressions of Improvement (CGI-Improvement) score of 1 or 2] were randomly assigned to continuation of CYMBALTA at the same dosage (N=216) or to placebo (N=213) and were observed for relapse. Of the patients randomized, 73% had been in a responder status for at least 10 weeks. Relapse was defined as an increase in CGI-Severity score at least 2 points to a score ≥4 and a MINI (Mini-International Neuropsychiatric Interview) diagnosis of GAD (excluding duration), or discontinuation due to lack of efficacy. Patients taking CYMBALTA experienced a statistically significantly longer time to relapse of GAD than did patients taking placebo (see Figure 2).

Subgroup analyses did not indicate that there were any differences in treatment outcomes as a function of age or gender.

GAD Trial in Geriatric Patients

The efficacy of CYMBALTA in the treatment of patients ≥65 years of age with GAD was established in one 10-week flexible-dose, randomized, double-blind, placebo-controlled trial in adults ≥65 years of age meeting the DSM-IV criteria for GAD (Study GAD-5). In Study GAD-5, the starting dose was 30 mg once daily for 2 weeks before further dose increases in 30 mg increments at treatment weeks 2, 4, and 7 up to 120 mg once daily were allowed based on investigator judgment of clinical response and tolerability. The mean dosage for patients completing the 10-week acute treatment phase was 51 mg. Patients treated with CYMBALTA (N=151) demonstrated significantly greater improvement compared with placebo (N=140) on mean change from baseline to endpoint as measured by the HAM-A total score (see Table 8).

GAD Trial in Pediatric Patients 7 to 17 Years Old

The efficacy of CYMBALTA in the treatment of pediatric patients 7 to 17 years of age with GAD was established in 1 flexible-dose randomized, double-blind, placebo-controlled trial in pediatric outpatients with GAD (based on DSM-IV criteria) (Study GAD-6).

In Study GAD-6, the starting dosage was 30 mg once daily for 2 weeks. Further dosage increases in 30 mg increments up to 120 mg once daily were allowed based on investigator judgment of clinical response and tolerability. The mean dosage for patients completing the 10-week treatment phase was 57.6 mg/day. In this study, CYMBALTA (N=135) demonstrated superiority over placebo (N=137) from baseline to endpoint as measured by greater improvement in the Pediatric Anxiety Rating Scale (PARS) for GAD severity score (see Table 9).

Table 9: Summary of the Primary Efficacy Results for GAD Trials
Study Number (population) (measurement) | Treatment Group | Primary Efficacy Measure
Study Number (population) (measurement) | Treatment Group | Mean Baseline Score (SD) | LS Mean Change from Baseline (SE) | Placebo-subtracted Differencea (95% CI)
Study GAD-1 (Adult) (HAM-A) | CYMBALTA (60 mg/day)b | 25.1 (7.18) | -12.8 (0.68) | -4.4 (-6.2, -2.5)
Study GAD-1 (Adult) (HAM-A) | CYMBALTA (120 mg/day)b | 25.1 (7.24) | -12.5 (0.67) | -4.1 (-5.9, -2.3)
Study GAD-1 (Adult) (HAM-A) | Placebo | 25.8 (7.66) | -8.4 (0.67) | --
Study GAD-2 (Adult) (HAM-A) | CYMBALTA (60-120 mg/day)b | 22.5 (7.44) | -8.1 (0.70) | -2.2 (-4.2, -0.3)
Study GAD-2 (Adult) (HAM-A) | Placebo | 23.5 (7.91) | -5.9 (0.70) | --
Study GAD-3 (Adult) (HAM-A) | CYMBALTA (60-120 mg/day)b | 25.8 (5.66) | -11.8 (0.69) | -2.6 (-4.5, -0.7)
Study GAD-3 (Adult) (HAM-A) | Placebo | 25.0 (5.82) | -9.2 (0.67) | --
Study GAD-5 (Geriatric) (HAM-A) | CYMBALTA (60-120 mg/day)b | 24.6 (6.21) | -15.9 (0.63) | -4.2 (-5.9, -2.5)
Study GAD-5 (Geriatric) (HAM-A) | Placebo | 24.5 (7.05) | -11.7 (0.67) | --
Study GAD-6 (Pediatric) (PARS for GAD) | CYMBALTA (30-120 mg/day)b | 17.5 (1.98) | -9.7 (0.50) | -2.7 (-4.0, -1.3)
Study GAD-6 (Pediatric) (PARS for GAD) | Placebo | 17.4 (2.24) | -7.1 (0.50) | --
SD: standard deviation; SE: standard error; LS Mean: least-squares mean; CI: confidence interval, not adjusted for multiplicity in trials where multiple dose groups were included.
a Difference (drug minus placebo) in least squares mean change from baseline.
b Dose statistically significantly superior to placebo.

Figure 2: Cumulative Proportiona of Adult Patients with GAD Relapse (Study GAD-4)

a Kaplan-Meier estimator method.

14.4 Diabetic Peripheral Neuropathic Pain in Adults

The efficacy of CYMBALTA for the management of neuropathic pain associated with diabetic peripheral neuropathy in adults was established in 2 randomized, 12-week, double-blind, placebo-controlled, fixed-dose trials in adult patients having diabetic peripheral neuropathic pain (DPNP) for at least 6 months (Study DPNP-1 and Study DPNP-2). These trials enrolled a total of 791 patients of whom 592 (75%) completed the trials. Patients enrolled had Type I or II diabetes mellitus with a diagnosis of painful distal symmetrical sensorimotor polyneuropathy for at least 6 months. The patients had a baseline pain score of ≥4 on an 11-point scale ranging from 0 (no pain) to 10 (worst possible pain). Patients were permitted up to 4 grams of acetaminophen per day as needed for pain, in addition to CYMBALTA. Patients recorded their pain daily in a diary.

Both trials compared CYMBALTA 60 mg once daily or 60 mg twice daily with placebo. Study DPNP-1 additionally compared CYMBALTA 20 mg with placebo. A total of 457 patients (342 CYMBALTA, 115 placebo) were enrolled in Study DPNP-1 and a total of 334 patients (226 CYMBALTA, 108 placebo) were enrolled in Study DPNP-2.

Treatment with CYMBALTA 60 mg one or two times a day statistically significantly improved the endpoint mean pain scores from baseline and increased the proportion of patients with at least a 50% reduction in pain scores from baseline. For various degrees of improvement in pain from baseline to study endpoint, Figures 3 and 4 show the fraction of patients achieving that degree of improvement in Studies DPNP-1 and DPNP-2, respectively. The figures are cumulative, so that patients whose change from baseline is, for example, 50%, are also included at every level of improvement below 50%. Patients who did not complete the trial were assigned 0% improvement. Some patients experienced a decrease in pain as early as week 1, which persisted throughout the trial.

Figure 3: Percentage of DPNP Adult Patients Achieving Various Levels of Pain Relief as Measured by 24-Hour Average Pain Severity (Study DPNP-1)

Figure 4: Percentage of DPNP Adult Patients Achieving Various Levels of Pain Relief as Measured by 24-Hour Average Pain Severity (Study DPNP-2)

14.5 Fibromyalgia

Adult Trials in Fibromyalgia

The efficacy of CYMBALTA for the management of fibromyalgia in adults was established in two randomized, double-blind, placebo-controlled, fixed-dose trials in adult patients meeting the American College of Rheumatology criteria for fibromyalgia (a history of widespread pain for 3 months, and pain present at 11 or more of the 18 specific tender point sites). Study FM-1 was three months in duration and enrolled female patients only. Study FM-2 was six months in duration and enrolled male and female patients. Approximately 25% of participants had a comorbid diagnosis of MDD. Studies FM-1 and FM-2 enrolled a total of 874 patients of whom 541 (62%) completed the trials. A total of 354 patients (234 CYMBALTA, 120 placebo) were enrolled in Study FM-1 and a total of 520 patients (376 CYMBALTA, 144 placebo) were enrolled in Study FM-2 (5% male, 95% female). The patients had a baseline pain score of 6.5 on an 11-point scale ranging from 0 (no pain) to 10 (worse possible pain).

Studies FM-1 and FM-2 compared CYMBALTA 60 mg once daily or 120 mg daily (given in divided doses in Study FM-1 and as a single daily dose in Study FM-2) with placebo. Study FM-2 additionally compared CYMBALTA 20 mg with placebo during the initial three months of a six-month trial.

Treatment with CYMBALTA 60 mg or 120 mg daily statistically significantly improved the endpoint mean pain scores from baseline and increased the proportion of patients with at least a 50% reduction in pain score from baseline. Pain reduction was observed in patients both with and without comorbid MDD. However, the degree of pain reduction may be greater in patients with comorbid MDD. For various degrees of improvement in pain from baseline to study endpoint, Figures 5 and 6 show the fraction of patients achieving that degree of improvement in Studies FM-1 and FM-2, respectively. The figures are cumulative so that patients whose change from baseline is, for example, 50%, are also included at every level of improvement below 50%. Patients who did not complete the trial were assigned 0% improvement. Some patients experienced a decrease in pain as early as week 1, which persisted throughout the trial. Improvement was also demonstrated on measures of function (Fibromyalgia Impact Questionnaires) and patient global impression of change (PGI). Neither trial demonstrated a benefit of 120 mg compared to 60 mg, and a higher dosage was associated with more adverse reactions and premature discontinuations of treatment.

Figure 5: Percentage of Adult Fibromyalgia Patients Achieving Various Levels of Pain Relief at Study Endpoint as Measured by 24-Hour Average Pain Severity (Study FM-1)

Figure 6: Percentage of Adult Fibromyalgia Patients Achieving Various Levels of Pain Relief at Study Endpoint as Measured by 24-Hour Average Pain Severity (Study FM-2)

Additionally, the benefit of up-titration in non-responders to CYMBALTA at 60 mg/day was evaluated in a separate trial (Study FM-3). Adult patients were initially treated with CYMBALTA 60 mg once daily for eight weeks in open-label fashion. Subsequently, completers of this phase were randomized to double-blind treatment with CYMBALTA at either 60 mg once daily or 120 mg once daily. Responders were defined as patients who had at least a 30% reduction in pain score from baseline at the end of the 8-week treatment. Patients who were non-responders at 8 weeks were no more likely to meet response criteria at the end of 60 weeks of treatment if blindly titrated to CYMBALTA 120 mg as compared to those who were blindly continued on CYMBALTA 60 mg.

Pediatric Trial in Fibromyalgia

CYMBALTA was studied in 184 pediatric patients aged 13 to 17 years with juvenile fibromyalgia syndrome in a 13-week, placebo-controlled trial (Study FM-4). In Study FM-4, 149 (81%) patients completed the trial. CYMBALTA (N=91) was initiated at a dosage of 30 mg once daily for one week and titrated to 60 mg once daily for 12 weeks, as tolerated. The mean dosage for patients completing the 12-week treatment phase was 49 mg/day. CYMBALTA showed improvement over placebo on the primary endpoint [change from baseline to end-of-treatment on the Brief Pain Inventory (BPI) – Modified Short Form: Adolescent Version 24-hour average pain severity rating] with a p-value of 0.052 from the pre-specified primary analysis, and p-values ranging from 0.011-0.020 from sensitivity analyses which assigned baseline values to missing assessments of some patients who did not complete the trial for various reasons. The patients had a baseline BPI of 5.7. For various degrees of improvement in pain from baseline to study endpoint, Figure 7 shows the fraction of patients achieving that degree of improvement in Study FM-4.

Figure 7: Percentage of Pediatric Patients Aged 13 to 17 Years Old with Juvenile Fibromyalgia Syndrome Achieving Various Levels of Pain Relief at Week 12 (Study FM-4) a

a Pain relief Measured by Brief Pain Inventory – Modified Short Form: Adolescent Version Average Pain Score.

b CYMBALTA-treated patients received 30 mg once daily for 1 week and subsequently titrated to 60 mg once daily for 12 weeks, as tolerated.

14.6 Chronic Musculoskeletal Pain in Adults

CYMBALTA is indicated for the treatment of chronic musculoskeletal pain in adults. This has been established in trials in adult patients with chronic low back pain and chronic pain due to osteoarthritis.

Trials in Chronic Low Back Pain in Adults

The efficacy of CYMBALTA in chronic low back pain (CLBP) in adults was assessed in two double-blind, placebo-controlled, randomized clinical trials of 13-weeks duration (Studies CLBP-1 and CLBP-2), and one of 12-weeks duration (CLBP-3). Studies CLBP-1 and CLBP-3 demonstrated efficacy of CYMBALTA in the treatment of CLBP. Patients in all trials had no signs of radiculopathy or spinal stenosis.

Study CLBP-1: Two hundred thirty-six adult patients (N=115 on CYMBALTA, N=121 on placebo) enrolled and 182 (77%) completed 13-week treatment phase. After 7 weeks of treatment, CYMBALTA-treated patients with less than 30% reduction in average daily pain and who were able to tolerate 60 mg once daily had their CYMBALTA dosage, in a double-blinded fashion, increased to 120 mg once daily for the remainder of the trial. Patients had a mean baseline pain rating of 6 on a numerical rating scale ranging from 0 (no pain) to 10 (worst possible pain). After 13 weeks of treatment, patients taking CYMBALTA 60-120 mg daily had a significantly greater pain reduction compared to patients taking placebo. Randomization was stratified by the patients' baseline NSAIDs use status. Subgroup analyses did not indicate that there were differences in treatment outcomes as a function of NSAIDs use.

Study CLBP-2: Four hundred and four patients were randomized to receive fixed dosages of CYMBALTA daily or a matching placebo (N=59 on CYMBALTA 20 mg, N=116 on CYMBALTA 60 mg, N=112 on CYMBALTA 120 mg, N=117 on placebo) and 267 (66%) completed the entire 13-week trial. After 13 weeks of treatment, none of the three CYMBALTA dosages showed a statistically significant difference in pain reduction compared to placebo.

Study CLBP-3: Four hundred and one patients were randomized to receive fixed doses of CYMBALTA 60 mg daily or placebo (N=198 on CYMBALTA, N=203 on placebo), and 303 (76%) completed the trial. Patients had a mean baseline pain rating of 6 on a numerical rating scale ranging from 0 (no pain) to 10 (worst possible pain). After 12 weeks of treatment, patients taking CYMBALTA 60 mg daily had significantly greater pain reduction compared to patients taking placebo.

For various degrees of improvement in pain from baseline to study endpoint, Figures 8 and 9 show the fraction of patients in Studies CLBP-1 and CLBP-3 achieving that degree of improvement, respectively. The figures are cumulative, so that patients whose change from baseline is, for example, 50%, are also included at every level of improvement below 50%. Patients who did not complete the trial were assigned the value of 0% improvement.

Figure 8: Percentage of Adult Patients with CLBP Achieving Various Levels of Pain Relief as Measured by 24-Hour Average Pain Severity (Study CLBP-1)

Figure 9: Percentage of Adult Patients with CLBP Achieving Various Levels of Pain Relief as Measured by 24-Hour Average Pain Severity (Study CLBP-3)

Trials in Chronic Pain Due to Osteoarthritis in Adults

The efficacy of CYMBALTA in chronic pain due to osteoarthritis (OA) in adults was assessed in 2 double-blind, placebo-controlled, randomized clinical trials of 13-weeks duration (Study OA-1 and Study OA-2). All patients in both trials fulfilled the ACR clinical and radiographic criteria for classification of idiopathic OA of the knee. Randomization was stratified by the patients' baseline NSAIDs-use status.

Patients assigned to CYMBALTA started treatment in both trials at a dose of 30 mg once daily for one week. After the first week, the dose of CYMBALTA was increased to 60 mg once daily. After 7 weeks of treatment with CYMBALTA 60 mg once daily, in Study OA-1 patients with sub-optimal response to treatment (<30% pain reduction) and tolerated CYMBALTA 60 mg once daily had their dose increased to 120 mg. However, in Study OA-2, all patients, regardless of their response to treatment after 7 weeks, were re-randomized to either continue receiving CYMBALTA 60 mg once daily or have their dosage increased to 120 mg once daily for the remainder of the trial. Patients in the placebo treatment groups in both trials received a matching placebo for the entire duration of trials. For both trials, efficacy analyses were conducted using 13-week data from the combined CYMBALTA 60 mg and 120 mg once daily treatment groups compared to the placebo group.

Study OA-1: Two hundred fifty-six patients (N=128 on CYMBALTA, N=128 on placebo) enrolled and 204 (80%) completed the trial. Patients had a mean baseline pain rating of 6 on a numerical rating scale ranging from 0 (no pain) to 10 (worst possible pain). After 13 weeks of treatment, patients taking CYMBALTA had significantly greater pain reduction than patients taking placebo. Subgroup analyses did not indicate that there were differences in treatment outcomes as a function of NSAIDs use.

Study OA-2: Two hundred thirty-one patients (N=111 on CYMBALTA, N=120 on placebo) enrolled and 173 (75%) completed the trial. Patients had a mean baseline pain of 6 on a numerical rating scale ranging from 0 (no pain) to 10 (worst possible pain). After 13 weeks of treatment, patients taking CYMBALTA did not show a significantly greater pain reduction than patients taking placebo.

In Study OA-1, for various degrees of improvement in pain from baseline to study endpoint, Figure 10 shows the fraction of patients achieving that degree of improvement. The figure is cumulative, so that patients whose change from baseline is, for example, 50%, are also included at every level of improvement below 50%. Patients who did not complete the trial were assigned the value of 0% improvement.

Figure 10: Percentage of Adult Patients with OA Achieving Various Levels of Pain Relief as Measured by 24-Hour Average Pain Severity (Study OA-1)

16 HOW SUPPLIED/STORAGE AND HANDLING

16.1 How Supplied

CYMBALTA (duloxetine delayed-release capsules) is available in the following strengths, colors, imprints, and presentations:

Features | Strengths
Features | 20 mga | 30 mga | 60 mga
Body color | Opaque green | Opaque white | Opaque green
Cap color | Opaque green | Opaque blue | Opaque blue
Cap imprint | Lilly 3235 | Lilly 3240 | Lilly 3270
Body imprint | 20mg | 30mg | 60mg
Capsule number | PU3235 | PU3240 | PU3270
Presentations and NDC Codes
Bottles of 30 | NA | 0002-3240-30 | 0002-3270-30
Bottles of 60 | 0002-3235-60 | NA | NA
Bottles of 90 | NA | 0002-3240-90 | NA
a equivalent to duloxetine base

16.2 Storage and Handling

Store at 25°C (77°F); excursions permitted to 15-30°C (59-86°F) [see USP Controlled Room Temperature].

17 PATIENT COUNSELING INFORMATION

Advise the patient to read the FDA-approved patient labeling (Medication Guide).

- Suicidal Thoughts and Behaviors — Advise patients, their families, and their caregivers to look for the emergence of suicidal ideation and behavior, especially during treatment and when the dose is adjusted up or down and instruct them to report such symptoms to their healthcare provider [see Boxed Warning and Warnings and Precautions (5.1)].
- Administration — Advise patients to swallow CYMBALTA whole and to not chew, crush, or open the capsule (do not sprinkle contents on food or mixed with liquids) because these actions might affect the enteric coating.
- Hepatotoxicity — Inform patients that severe liver problems, sometimes fatal, have been reported in patients treated with CYMBALTA. Instruct patients to talk to their healthcare provider if they develop itching, right upper belly pain, dark urine, or yellow skin/eyes while taking CYMBALTA, which may be signs of liver problems. Instruct patients to talk to their healthcare provider about their alcohol consumption. Use of CYMBALTA with heavy alcohol intake may be associated with severe liver injury [see Warnings and Precautions (5.2)].
- Alcohol — Although CYMBALTA does not increase the impairment of mental and motor skills caused by alcohol, use of CYMBALTA concomitantly with heavy alcohol intake may be associated with severe liver injury [see Warnings and Precautions (5.2) and Drug Interactions (7.15)].
- Orthostatic Hypotension, Falls and Syncope — Advise patients of the risk of orthostatic hypotension, falls and syncope, especially during the period of initial use and subsequent dose escalation, and in association with the use of concomitant drugs that might potentiate the orthostatic effect of CYMBALTA [see Warnings and Precautions (5.3)].
- Serotonin Syndrome — Caution patients about the risk of serotonin syndrome with the concomitant use of CYMBALTA and other serotonergic agents including triptans, tricyclic antidepressants, opioids, lithium, buspirone, tryptophan, amphetamines, and St. John's Wort [see Contraindications (4), Warnings and Precautions (5.4), and Drug Interactions (7.14)]. Advise patients of the signs and symptoms associated with serotonin syndrome that may include mental status changes (e.g., agitation, hallucinations, delirium, and coma), autonomic instability (e.g., tachycardia, labile blood pressure, dizziness, diaphoresis, flushing, hyperthermia), neuromuscular changes (e.g., tremor, rigidity, myoclonus, hyperreflexia, incoordination), seizures, and/or gastrointestinal symptoms (e.g., nausea, vomiting, diarrhea). Caution patients to seek medical care immediately if they experience these symptoms.
- Increased Risk of Bleeding — Caution patients about the concomitant use of CYMBALTA and NSAIDs, aspirin, warfarin, or other drugs that affect coagulation since combined use of psychotropic drugs that interfere with serotonin reuptake and these agents has been associated with an increased risk of bleeding [see Warnings and Precautions (5.5) and Use in Specific Populations (8.1)].
- Severe Skin Reactions — Caution patients that CYMBALTA may cause serious skin reactions. This may need to be treated in a hospital and may be life-threatening. Counsel patients to call their doctor right away or get emergency help if they have skin blisters, peeling rash, sores in their mouth, hives, or any other allergic reactions [see Warnings and Precautions (5.6)].
- Discontinuation of Treatment — Instruct patients that discontinuation of CYMBALTA may be associated with symptoms such as dizziness, headache, nausea, diarrhea, paresthesia, irritability, vomiting, insomnia, anxiety, hyperhidrosis, and fatigue, and should be advised not to alter their dosing regimen, or stop taking CYMBALTA without consulting their healthcare provider [see Warnings and Precautions (5.7)].
- Activation of Mania or Hypomania — Adequately screen patients with depressive symptoms for risk of bipolar disorder (e.g. family history of suicide, bipolar disorder, and depression) prior to initiating treatment with CYMBALTA. Advise patients to report any signs or symptoms of a manic reaction such as greatly increased energy, severe trouble sleeping, racing thoughts, reckless behavior, talking more or faster than usual, unusually grand ideas, and excessive happiness or irritability [see Warnings and Precautions (5.8)].
- Angle-Closure Glaucoma — Advise patients that taking CYMBALTA can cause mild pupillary dilation, which in susceptible individuals, can lead to an episode of angle-closure glaucoma. Pre-existing glaucoma is almost always open-angle glaucoma because angle-closure glaucoma, when diagnosed, can be treated definitively with iridectomy. Open-angle glaucoma is not a risk factor for angle-closure glaucoma. Patients may wish to be examined to determine whether they are susceptible to angle-closure, and have a prophylactic procedure (e.g., iridectomy), if they are susceptible [see Warnings and Precautions (5.9)].
- Seizures — Advise patients to inform their healthcare provider if they have a history of seizure disorder [see Warnings and Precautions (5.10)].
- Effects on Blood Pressure — Caution patients that CYMBALTA may cause an increase in blood pressure [see Warnings and Precautions (5.11)].
- Concomitant Medications — Advise patients to inform their healthcare provider if they are taking, or plan to take, any prescription or over-the-counter medications, since there is a potential for interactions [see Dosage and Administration (2.9, 2.10), Contraindications (4), Warnings and Precautions (5.4, 5.12), and Drug Interactions (7)].
- Hyponatremia — Advise patients that hyponatremia has been reported as a result of treatment with SNRIs and SSRIs, including CYMBALTA. Advise patients of the signs and symptoms of hyponatremia [see Warnings and Precautions (5.13)].
- Concomitant Illnesses — Advise patients to inform their healthcare provider about all of their medical conditions [see Warnings and Precautions (5.14)].
- Urinary Hesitation and Retention — CYMBALTA is in a class of medicines that may affect urination. Instruct patients to consult with their healthcare provider if they develop any problems with urine flow [see Warnings and Precautions (5.15)].
- Sexual Dysfunction — Advise patients that use of CYMBALTA may cause symptoms of sexual dysfunction in both male and female patients. Inform patients that they should discuss any changes in sexual function and potential management strategies with their healthcare provider [see Warnings and Precautions (5.16)].
- Pregnancy
  - Advise women to notify their healthcare provider if they become pregnant or intend to become pregnant during treatment with CYMBALTA.
  - Advise pregnant women or patients who intend to become pregnant that CYMBALTA may increase the risk of neonatal complications requiring prolonged hospitalization, respiratory support, and tube feeding.
  - Advise pregnant women that there is a risk of relapse with discontinuation of antidepressants.
  - Advise patients that there is a pregnancy exposure registry that monitors pregnancy outcomes in women exposed to CYMBALTA during pregnancy [see Use in Specific Populations (8.1)].
- Lactation — Advise breastfeeding women using CYMBALTA to monitor infants for sedation, poor feeding and poor weight gain and to seek medical care if they notice these signs [see Use in Specific Populations (8.2)].
- Interference with Psychomotor Performance — CYMBALTA may be associated with sedation and dizziness. Therefore, caution patients about operating hazardous machinery including automobiles, until they are reasonably certain that CYMBALTA therapy does not affect their ability to engage in such activities.

Marketed by: Lilly USA, LLC, Indianapolis, IN 46285, USA

Copyright © 2004, 2023, Eli Lilly and Company. All rights reserved.

CYM-0014-USPI-20230818

Medication Guide

Cymbalta®
[sim-BALL-tah]
(duloxetine delayed-release capsules)

Read this Medication Guide before you start taking Cymbalta® and each time you get a refill. There may be new information. This information does not take the place of talking to your healthcare provider about your medical condition or treatment.

Talk to your healthcare provider about:

- all risks and benefits of treatment with antidepressant medicines
- all treatment choices for depression or other serious mental illness

What is the most important information I should know about antidepressant medicines, depression, other serious mental illnesses, and suicidal thoughts or actions?

1. Cymbalta and other antidepressant medicines may increase suicidal thoughts or actions in some children, teenagers, or young adults within the first few months of treatment or when the dose is changed.

2. Depression and other serious mental illnesses are the most important causes of suicidal thoughts or actions. Some people may have a particularly high risk of having suicidal thoughts or actions. These include people who have (or have a family history of) bipolar illness (also called manic-depressive illness).

3. How can I watch for and try to prevent suicidal thoughts and actions?

- Pay close attention to any changes in mood, behavior, actions, thoughts, or feelings, especially sudden changes. This is very important when an antidepressant medicine is started or when the dose is changed.
- Call your healthcare provider right away to report new or sudden changes in mood, behavior, thoughts, or feelings.
  - Keep all follow-up visits with your healthcare provider as scheduled. Call your healthcare provider between visits as needed, especially if you have concerns about symptoms.

Call your healthcare provider right away if you have any of the following symptoms or feelings, especially if they are new, worse, or worry you. In an emergency, call 911.

- attempts to commit suicide
- acting on dangerous impulses
- acting aggressive, being angry, or violent
- thoughts about suicide or dying
- new or worse depression
- new or worse anxiety
- panic attacks
- feeling very agitated or restless
- new or worse irritability
- trouble sleeping
- an extreme increase in activity or talking (mania)
- other unusual changes in behavior or mood

What else do I need to know about antidepressant medicines?

- Never stop an antidepressant medicine without first talking to a healthcare provider. Stopping an antidepressant medicine suddenly can cause other symptoms.
- Antidepressants are medicines used to treat depression and other illnesses. It is important to discuss all the risks of treating depression and also the risks of not treating it. Patients should discuss all treatment choices with your healthcare provider, not just the use of antidepressants.
- Antidepressant medicines have other side effects. Talk to your healthcare provider about the side effects of the medicine prescribed for you or your family member.
- Antidepressant medicines can interact with other medicines. Know all of the medicines that you or your family member takes. Keep a list of all medicines to show your healthcare provider. Do not start new medicines without first checking with your healthcare provider.

What is Cymbalta?

Cymbalta is a prescription medicine used to treat a certain type of depression called Major Depressive Disorder (MDD). Cymbalta belongs to a class of medicines known as SNRIs (or serotonin-norepinephrine reuptake inhibitors).

Cymbalta is also used to treat or manage:

- Generalized Anxiety Disorder (GAD)
- Diabetic Peripheral Neuropathic Pain (DPNP)
- Fibromyalgia (FM)
- Chronic Musculoskeletal Pain

Who should not take Cymbalta?

Do Not take Cymbalta if you:

- take a Monoamine Oxidase Inhibitor (MAOI). Ask your healthcare provider or pharmacist if you are not sure if you take an MAOI, including the antibiotic linezolid or intravenous methylene blue.
  - Do not take an MAOI within 5 days of stopping Cymbalta unless directed to do so by your healthcare provider.
  - Do not start Cymbalta if you stopped taking an MAOI in the last 14 days unless directed to do so by your healthcare provider.

People who take Cymbalta close in time to an MAOI may have a serious problem called Serotonin Syndrome (see “What are the possible side effects of Cymbalta?”).

What should I tell my healthcare provider before taking Cymbalta?

Before starting Cymbalta, tell your healthcare provider if you:

- have heart problems or high blood pressure
- have diabetes (Cymbalta treatment makes it harder for some people with diabetes to control their blood sugar)
- have liver problems
- have kidney problems
- have glaucoma
- have or had seizures or convulsions
- have bipolar disorder or mania
- have low sodium levels in your blood
- have delayed stomach emptying
- have or had bleeding problems
- are pregnant or plan to become pregnant. Cymbalta may harm your unborn baby. Talk to your healthcare provider about the risk to your unborn baby if you take Cymbalta during pregnancy.
  - Tell your healthcare provider right away if you become pregnant or think you are pregnant during treatment with Cymbalta.
  - There is a pregnancy registry for females who are exposed to Cymbalta during pregnancy. The purpose of the registry is to collect information about the health of females exposed to Cymbalta and their baby. If you become pregnant during treatment with Cymbalta, talk to your healthcare provider about registering with the National Pregnancy Registry for Antidepressants at 1-866-961-2388 or visit online at
    https://womensmentalhealth.org/research/pregnancyregistry/.
- are breastfeeding or plan to breastfeed. Cymbalta passes into your breast milk and may harm your baby. Talk to your healthcare provider about the best way to feed your baby while taking Cymbalta.

Tell your healthcare provider about all the medicines that you take, including prescription and over-the-counter medicines, vitamins, and herbal supplements. Cymbalta and some medicines may interact with each other, may not work as well, or may cause serious side effects.

Especially tell your healthcare provider if you take:

- triptans used to treat migraine headache
- medicines used to treat mood, anxiety, psychotic or thought disorders, including tricyclics, lithium, buspirone, SSRIs, SNRIs or MAOIs
- tramadol, fentanyl, meperidine, methadone, or other opioids
- amphetamines
- cimetidine
- the antibiotics ciprofloxacin, enoxacin
- medicine to treat irregular heart rate (like propafenone, flecainide, quinidine)
- theophylline
- the blood thinner warfarin (Coumadin, Jantoven)
- non-steroidal anti-inflammatory drug (NSAID) (like ibuprofen, naproxen or aspirin).
- over-the-counter supplements such as tryptophan or St. John’s Wort
- thioridazine (Mellaril). Mellaril together with Cymbalta can cause serious heart rhythm problems or sudden death.

Ask your healthcare provider for a list of these medicines if you are not sure.

Do not take Cymbalta with any other medicine that contain duloxetine.

How should I take Cymbalta?

- Take Cymbalta exactly as your healthcare provider tells you to take it. Your healthcare provider may need to change the dose of Cymbalta until it is the right dose for you.
- Swallow Cymbalta whole. Do not chew or crush Cymbalta.
- Do not open the capsule and sprinkle on food or mix with liquids. Opening the capsule may affect how well Cymbalta works.
- Cymbalta may be taken with or without food.
- If you miss a dose of Cymbalta, take the missed dose as soon as you remember. If it is almost time for the next dose, skip the missed dose and take your next dose at the regular time. Do not take two doses of Cymbalta at the same time.
- If you take too much Cymbalta, call your healthcare provider or poison control center at 1-800-222-1222 right away, or get emergency treatment.
- When switching from another antidepressant to Cymbalta your healthcare provider may want to lower the dose of the initial antidepressant first to potentially avoid side effects.

What should I avoid while taking Cymbalta?

- Cymbalta can cause sleepiness or may affect your ability to make decisions, think clearly, or react quickly. You should not drive, operate heavy machinery, or do other dangerous activities until you know how Cymbalta affects you.
- Use of Cymbalta concomitantly with heavy alcohol intake may be associated with severe liver injury. Avoid heavy alcohol use while taking Cymbalta.

What are the possible side effects of Cymbalta?

Cymbalta may cause serious side effects, including: See “What is the most important information I should know about Cymbalta?”

Common possible side effects in people who take Cymbalta include:

1. liver damage. Symptoms may include:

- itching
- right upper abdominal pain
- dark urine
- yellow skin or eyes
- enlarged liver
- increased liver enzymes

2. changes in blood pressure and falls. Monitor your blood pressure before starting and throughout treatment. Cymbalta may:

- increase your blood pressure.
- decrease your blood pressure when standing and cause dizziness or fainting, mostly when first starting Cymbalta or when increasing the dose.
- increase risk of falls, especially in elderly.

3. Serotonin Syndrome: This condition can be life-threatening and symptoms may include:

- agitation, hallucinations, coma or other changes in mental status
- coordination problems or muscle twitching (overactive reflexes)
- racing heartbeat, high or low blood pressure
- sweating or fever
- nausea, vomiting, or diarrhea
- muscle rigidity
- dizziness
- flushing
- tremor
- seizures

4. abnormal bleeding: Cymbalta and other antidepressant medicines may increase your risk of bleeding or bruising, especially if you take the blood thinner warfarin (Coumadin, Jantoven), a non-steroidal anti-inflammatory drug (NSAIDs, like ibuprofen or naproxen), or aspirin.

5. severe skin reactions: Cymbalta may cause serious skin reactions that may require stopping its use. This may need to be treated in a hospital and may be life-threatening. Call your healthcare provider right away or get emergency help if you have skin blisters, peeling rash, sores in the mouth, hives or any other allergic reactions.

6. discontinuation symptoms: Do not stop Cymbalta without first talking to your healthcare provider. Stopping Cymbalta too quickly or changing from another antidepressant too quickly may result in serious symptoms including:

- anxiety
- irritability
- feeling tired or problems sleeping
- headache
- sweating
- dizziness
- electric shock-like sensations
- vomiting or nausea
- diarrhea

7. manic episodes:

- greatly increased energy
- severe trouble sleeping
- racing thoughts
- reckless behavior
- unusually grand ideas
- excessive happiness or irritability
- talking more or faster than usual

8. visual problems:

- eye pain
- changes in vision
- swelling or redness in or around the eye

Only some people are at risk for these problems. You may want to undergo an eye examination to see if you are at risk and receive preventative treatment if you are.

9. seizures or convulsions

10. low salt (sodium) levels in the blood. Elderly people may be at greater risk for this. Symptoms may include:

- headache
- weakness or feeling unsteady
- confusion, problems concentrating or thinking or memory problems

11. problems with urination. Symptoms may include:

- decreased urine flow
- unable to pass any urine

12. sexual problems (dysfunction). Taking serotonin and norepinephrine reuptake inhibitors (SNRIs), including CYMBALTA, may cause sexual problems.

Symptoms in males may include:

- delayed ejaculation or inability to have an ejaculation
- decreased sex drive
- problems getting or keeping an erection

Symptoms in females may include:

- decreased sex drive
- delayed orgasm or inability to have an orgasm

Talk to your healthcare provider if you develop any changes in your sexual function or if you have any questions or concerns about sexual problems during treatment with CYMBALTA. There may be treatments your healthcare provider can suggest.

The most common side effects of Cymbalta include:

- nausea
- dry mouth
- sleepiness
- fatigue
- constipation
- loss of appetite
- increased sweating
- dizziness

Common possible side effects in children and adolescents who take Cymbalta include:

- nausea
- decreased weight
- dizziness

Side effects in adults may also occur in children and adolescents who take Cymbalta. Children and adolescents should have height and weight monitored during treatment.

Tell your healthcare provider if you have any side effect that bothers you or that does not go away. These are not all the possible side effects of Cymbalta. For more information, ask your healthcare provider or pharmacist.

Call your doctor for medical advice about side effects. You may report side effects to 1-800-FDA-1088.

How should I store Cymbalta?

Store Cymbalta at room temperature between 68°F to 77°F (20°C to 25°C).

Keep Cymbalta and all medicines out of the reach of children.

General information about the safe and effective use of Cymbalta.

Medicines are sometimes prescribed for purposes other than those listed in a Medication Guide. Do not use Cymbalta for a condition for which it was not prescribed. Do not give Cymbalta to other people, even if they have the same symptoms that you have. It may harm them.

This Medication Guide summarizes the most important information about Cymbalta. If you would like more information, talk with your healthcare provider. You may ask your healthcare provider or pharmacist for information about Cymbalta that is written for healthcare professionals.

For more information, call 1-800-545-5979.

What are the ingredients in Cymbalta?

Active ingredient: duloxetine hydrochloride

Inactive ingredients:

FD&C Blue No. 2, gelatin, hypromellose, hydroxypropyl methylcellulose acetate succinate, sodium lauryl sulfate, sucrose, sugar spheres, talc, titanium dioxide, and triethyl citrate. The 20 and 60 mg capsules also contain iron oxide yellow.

This Medication Guide has been approved by the U.S. Food and Drug Administration.

Coumadin, Jantoven, and Mellaril are trademarks of their respective owners and not trademarks of Eli Lilly and Company.

Medication Guide revised: 08/2023

Marketed by: Lilly USA, LLC
Indianapolis, IN 46285, USA

Cymbalta is a registered trademark of Eli Lilly and Company.

Copyright © 2009, 2023, Eli Lilly and Company. All rights reserved.

CYM-0007-MG-20230818

PACKAGE LABEL- Cymbalta 20 mg, bottle of 60

NDC 0002-3235-60

60 capsules

PU3235

Cymbalta®

duloxetine

delayed release capsules

20 mg

Each capsule contains 22.4 mg of duloxetine hydrochloride equivalent to 20 mg duloxetine.

Rx only

Lilly

PACKAGE LABEL- Cymbalta 30 mg, bottle of 30

NDC 0002-3240-30

30 capsules

PU3240

Cymbalta®

duloxetine

delayed release capsules

30 mg

Each capsule contains 33.7 mg of duloxetine hydrochloride equivalent to 30 mg duloxetine.

Rx only

Lilly

PACKAGE LABEL- Cymbalta 60 mg, bottle of 30

NDC 0002-3270-30

30 capsules

PU3270

Cymbalta®

duloxetine

delayed release capsules

60 mg

Each capsule contains 67.3 mg of duloxetine hydrochloride equivalent to 60 mg duloxetine.

Rx only

Lilly